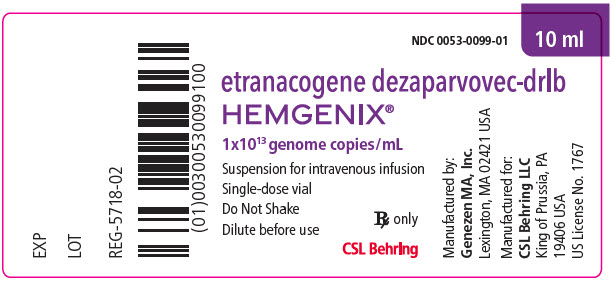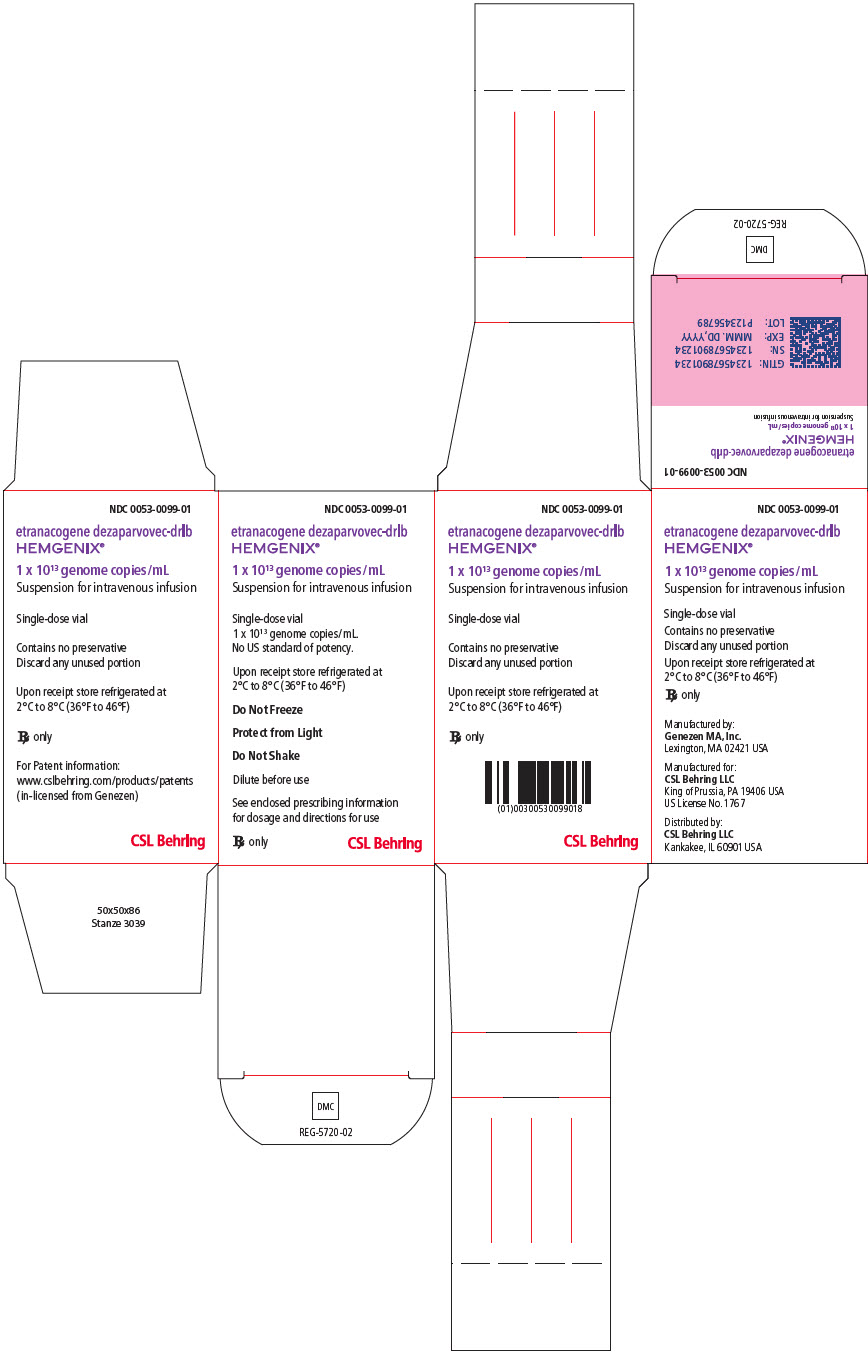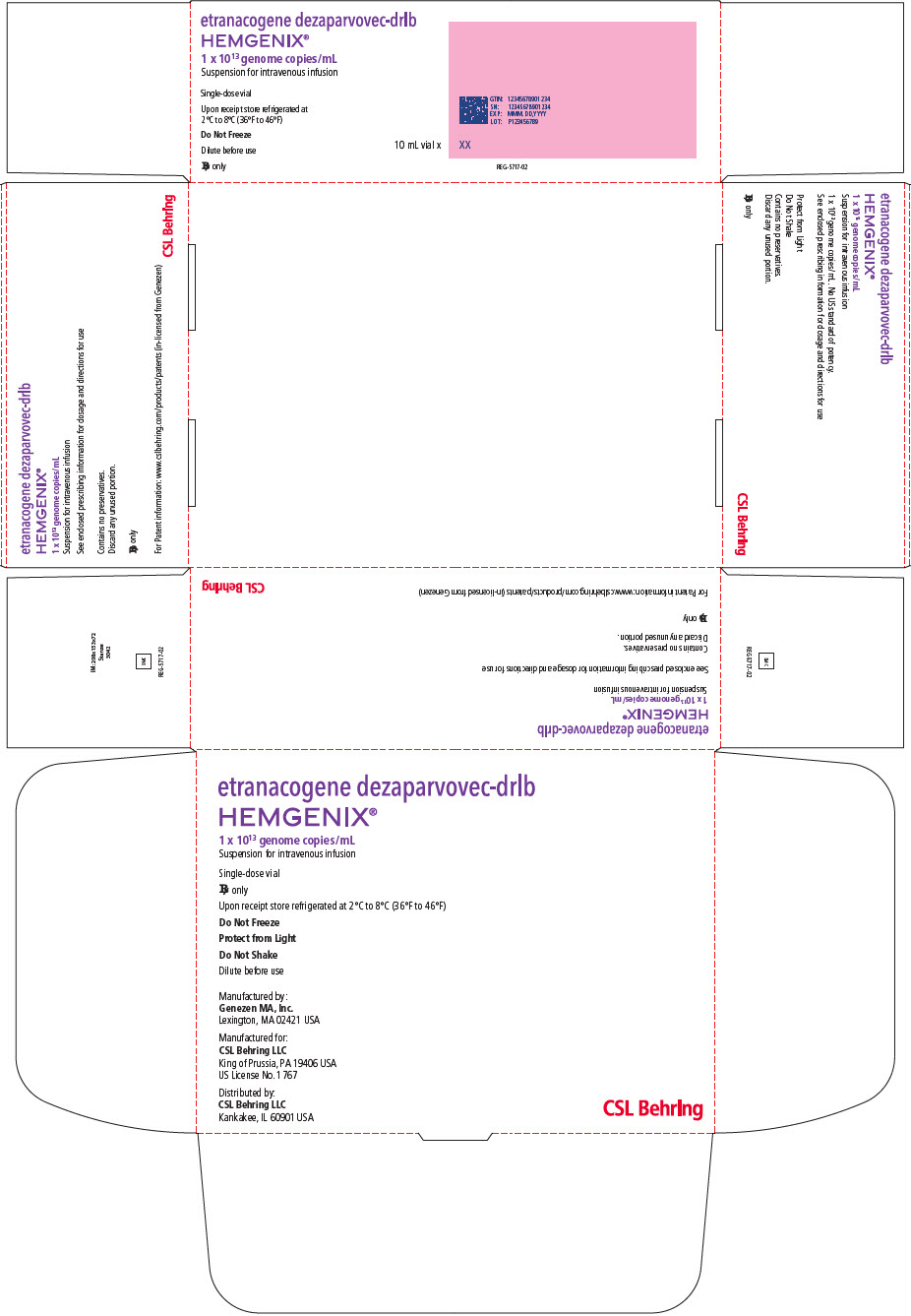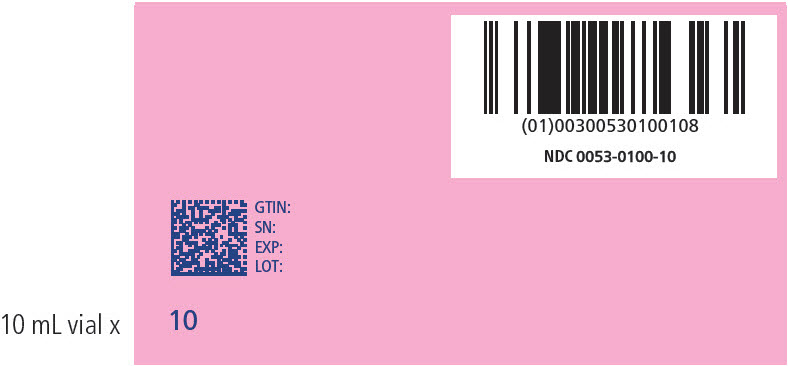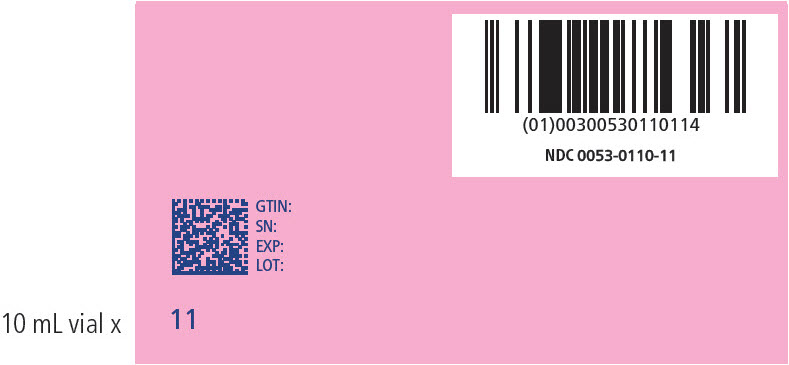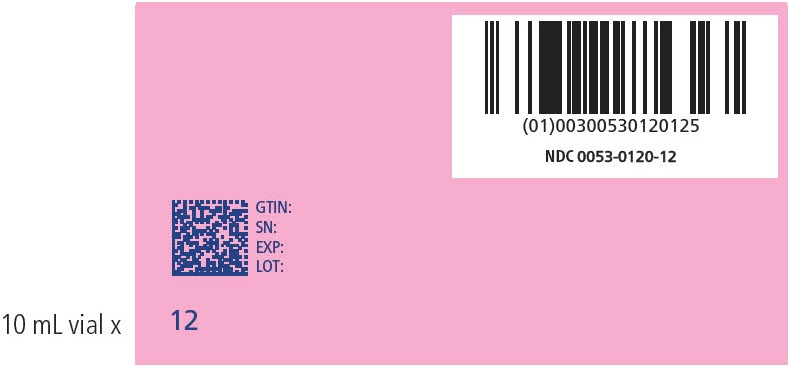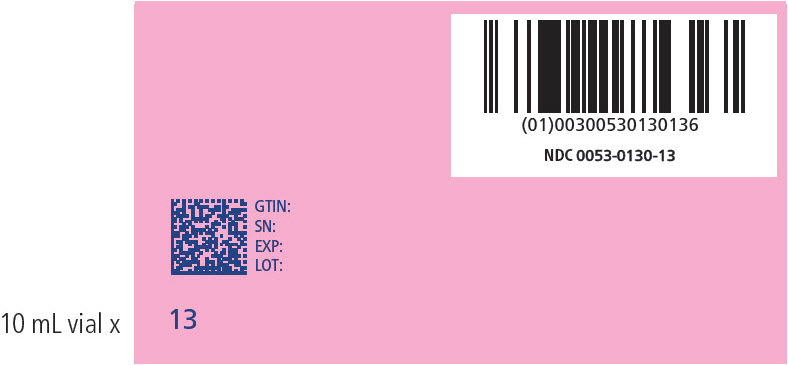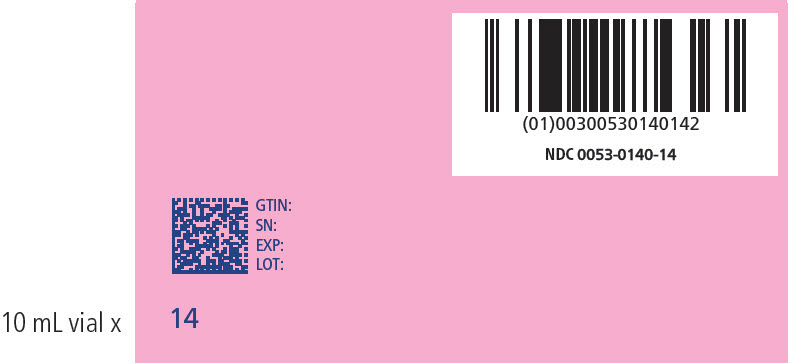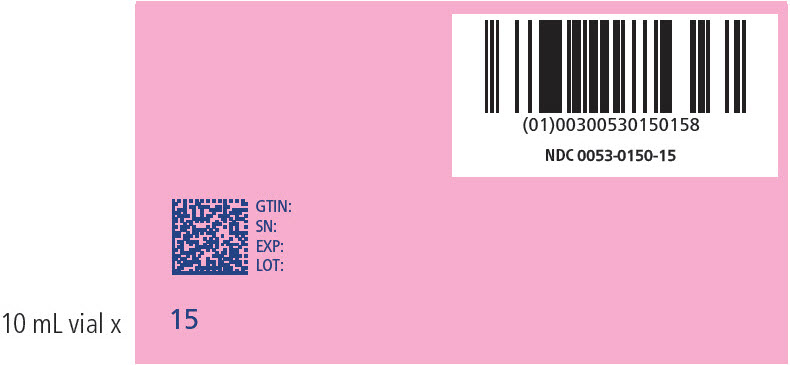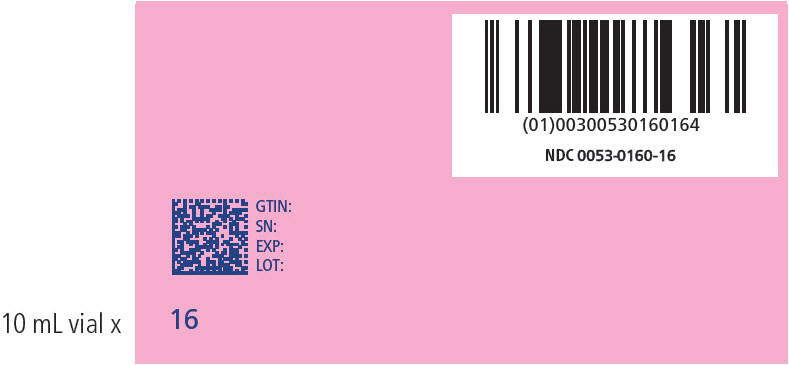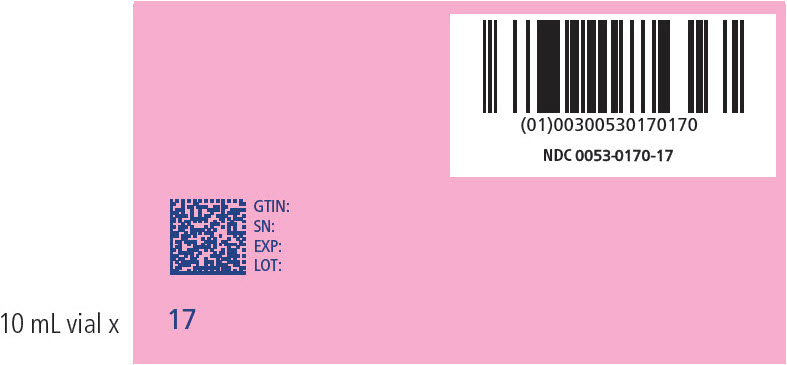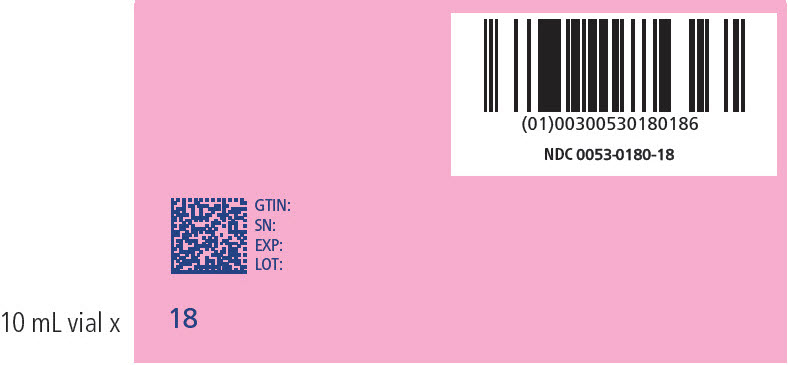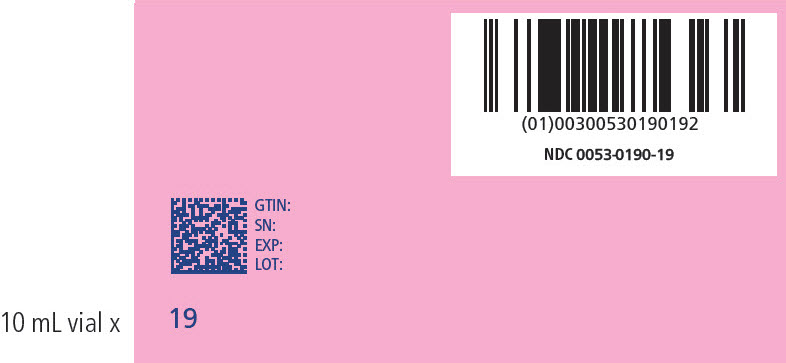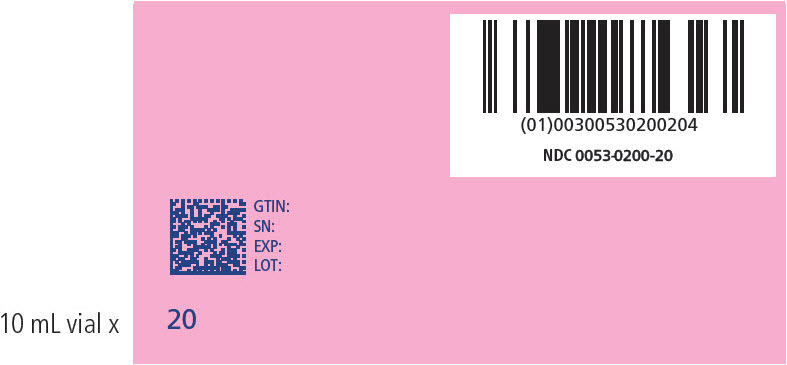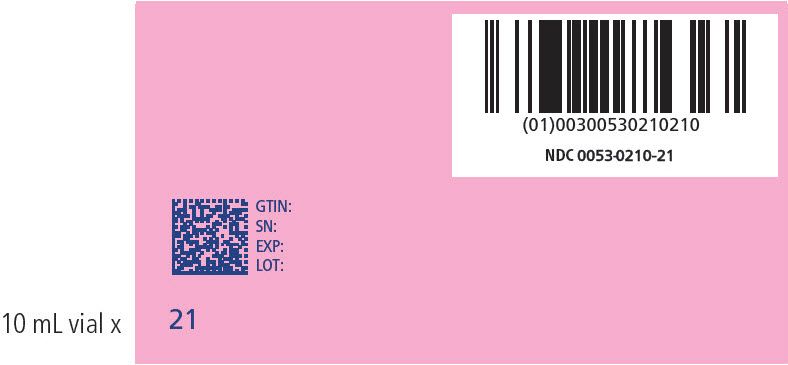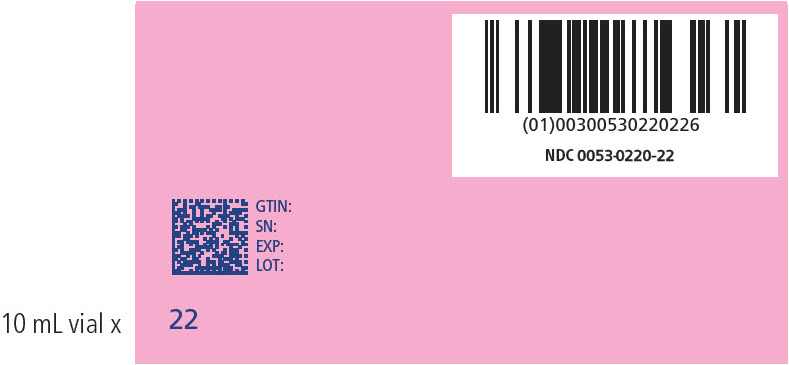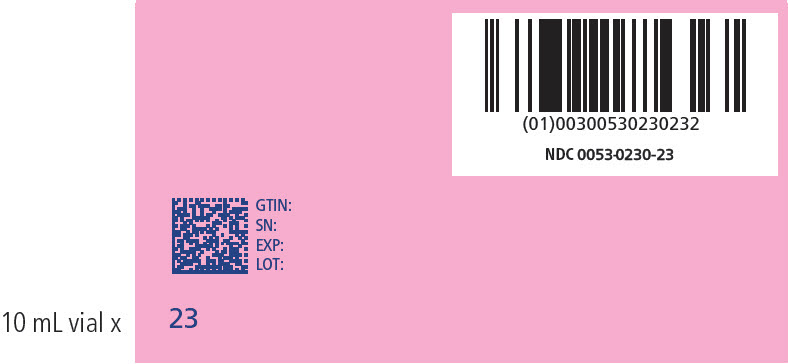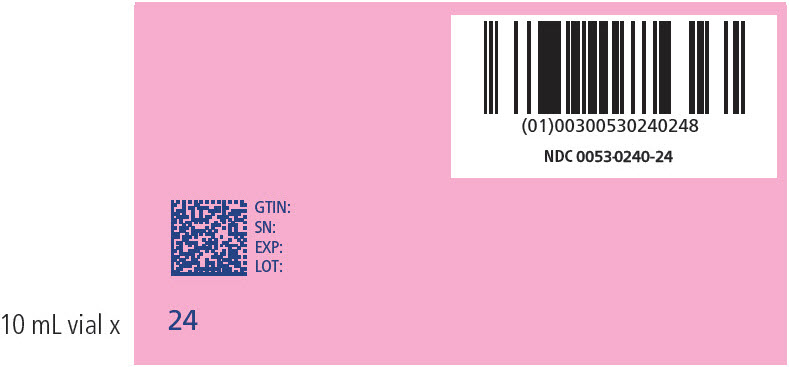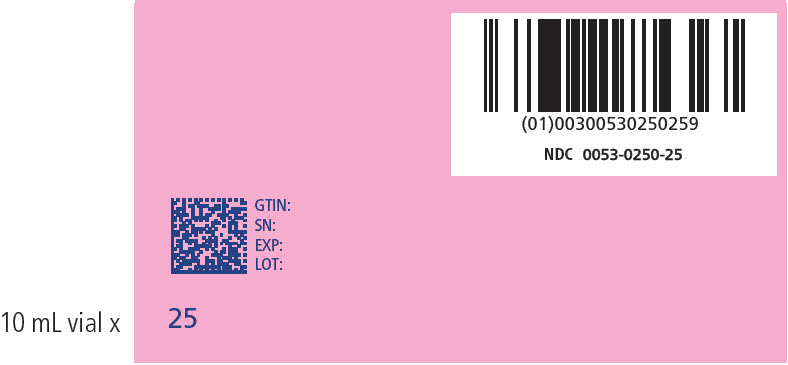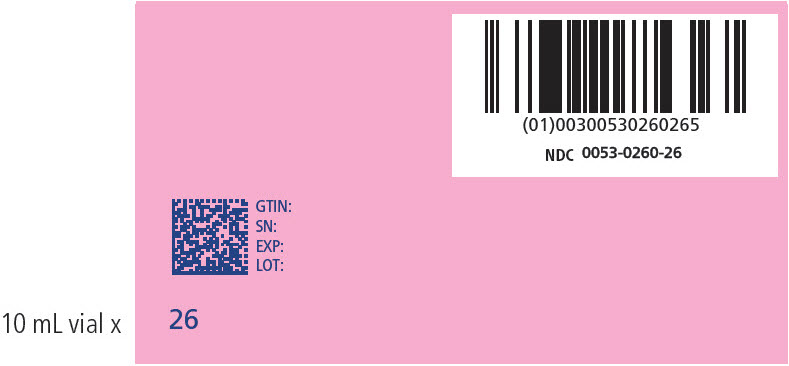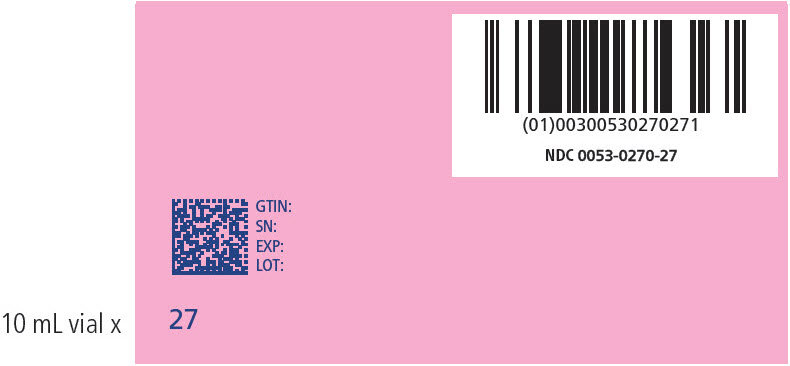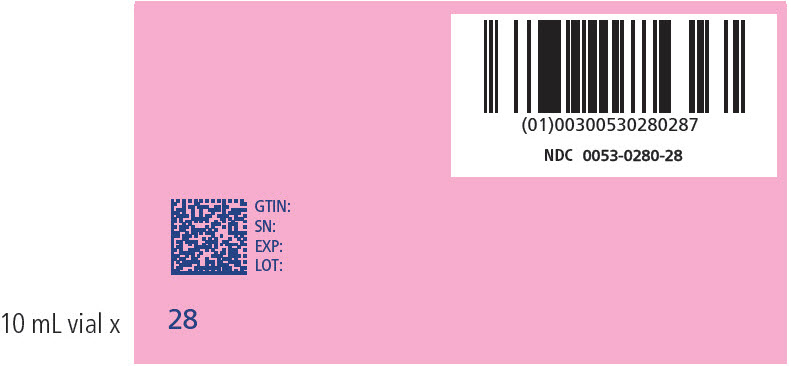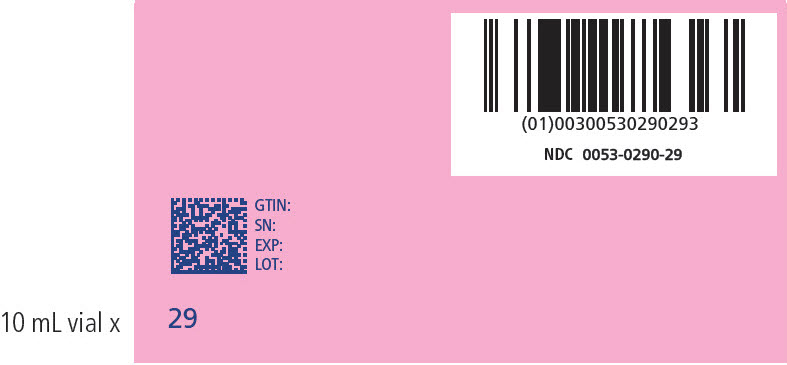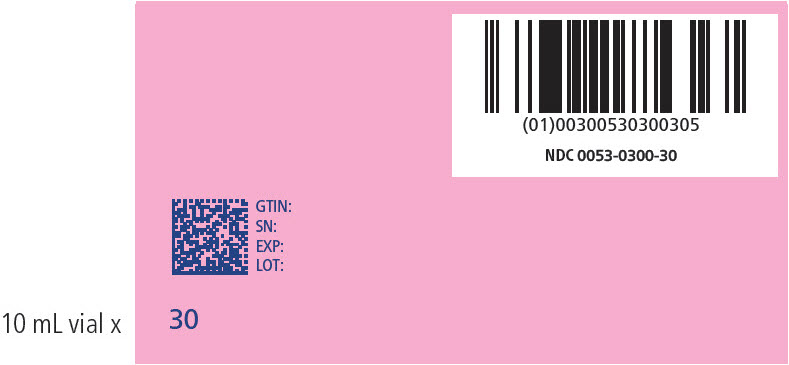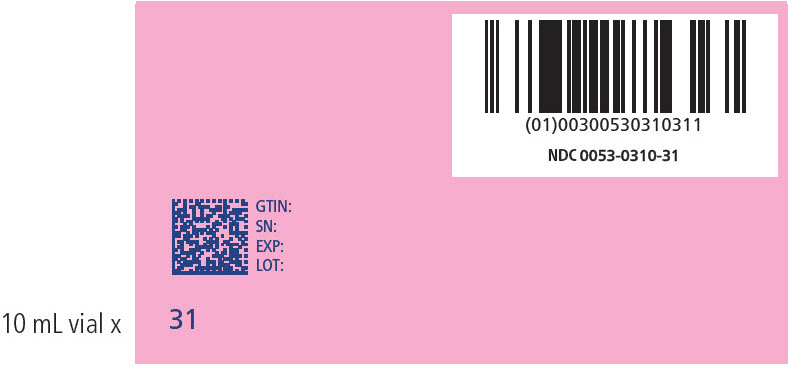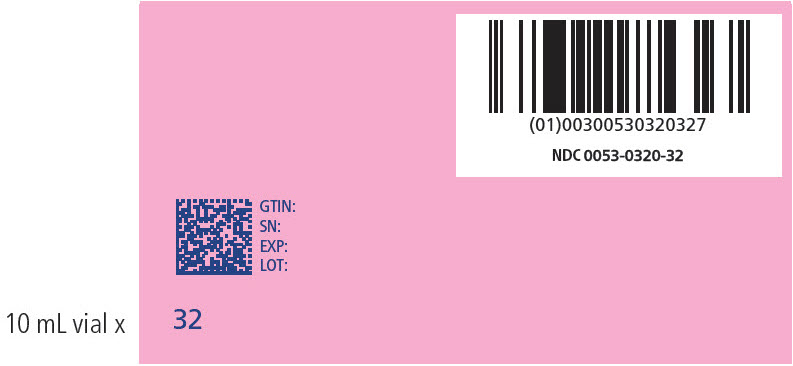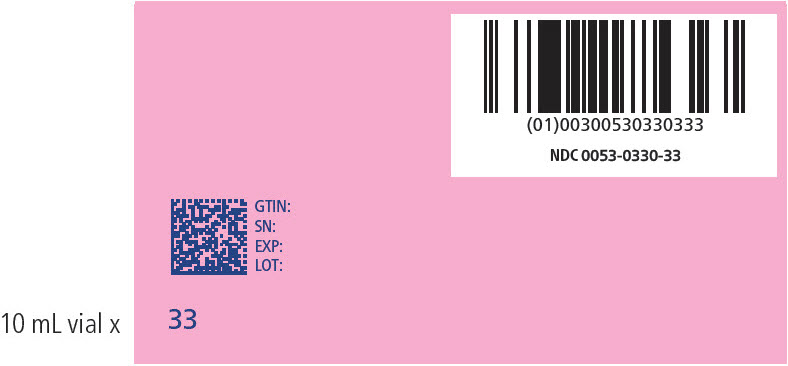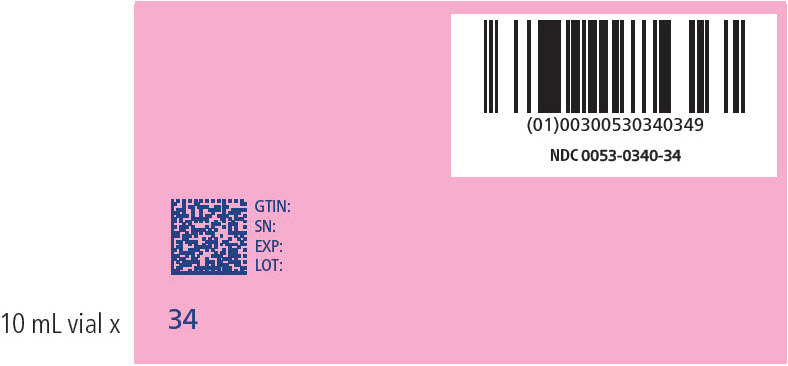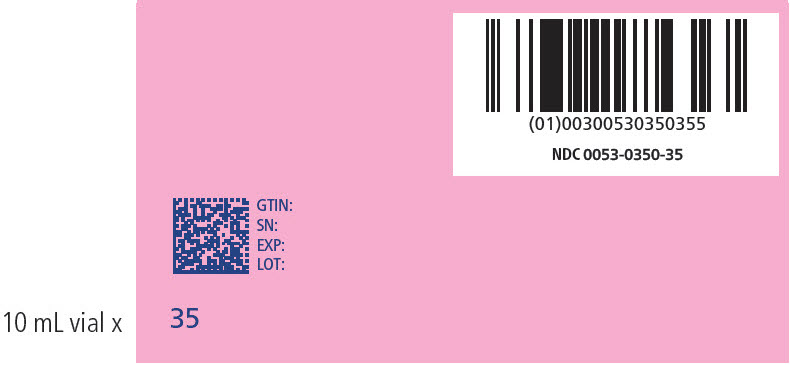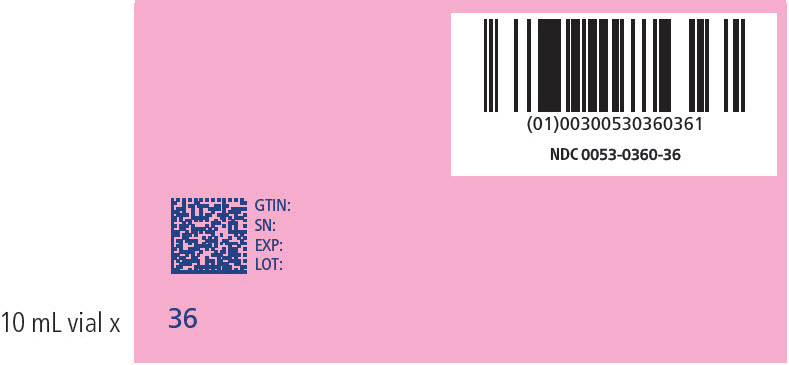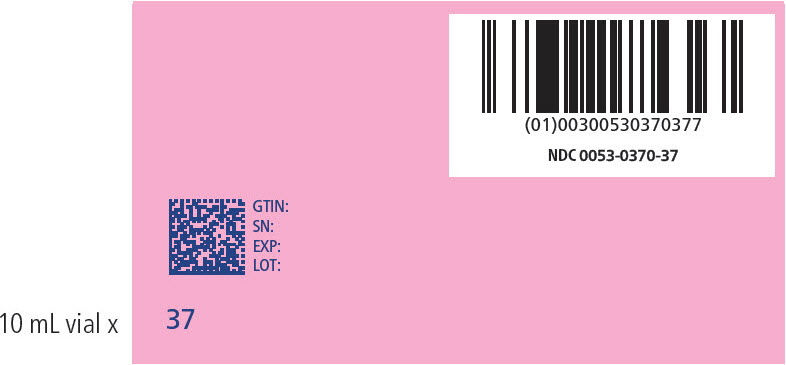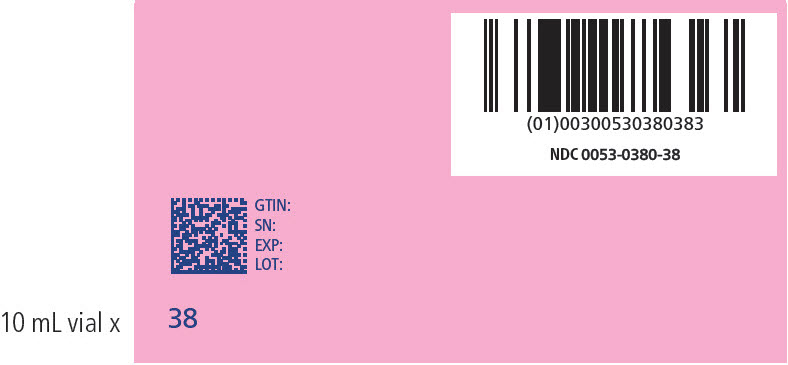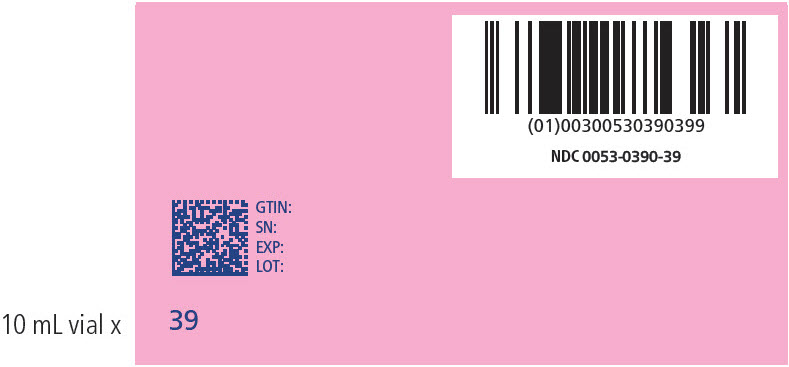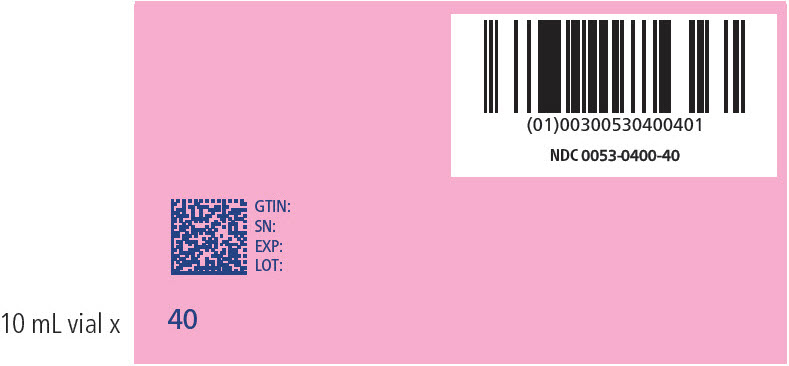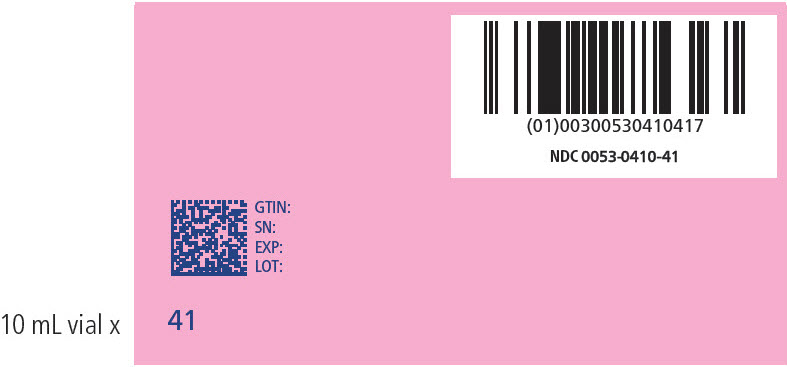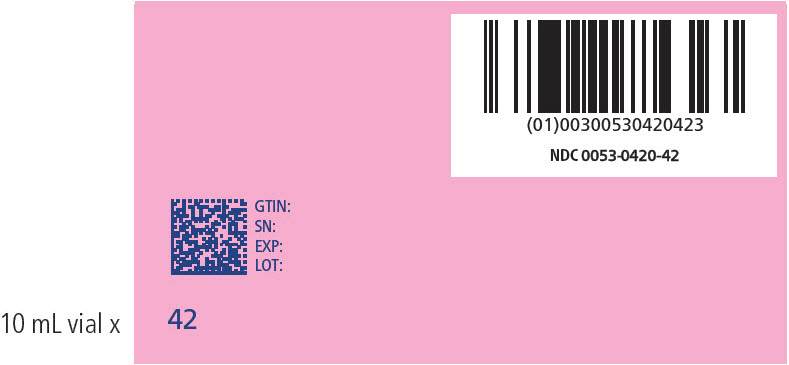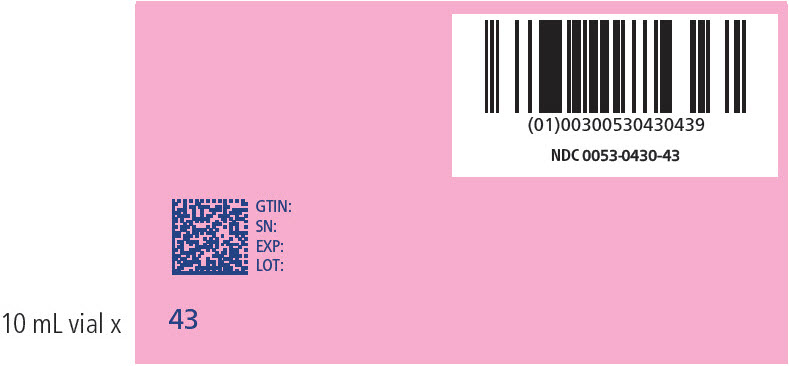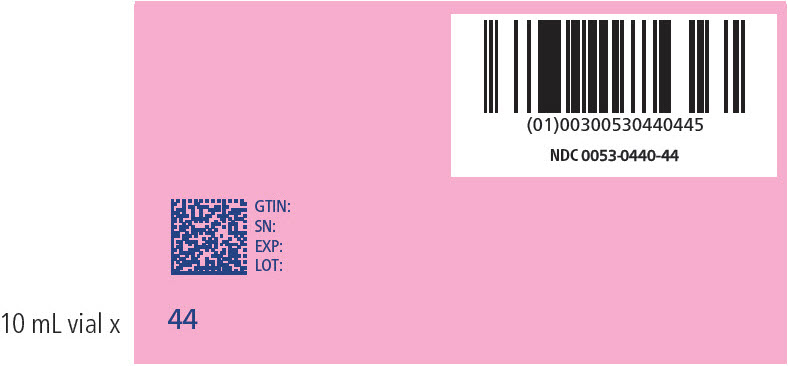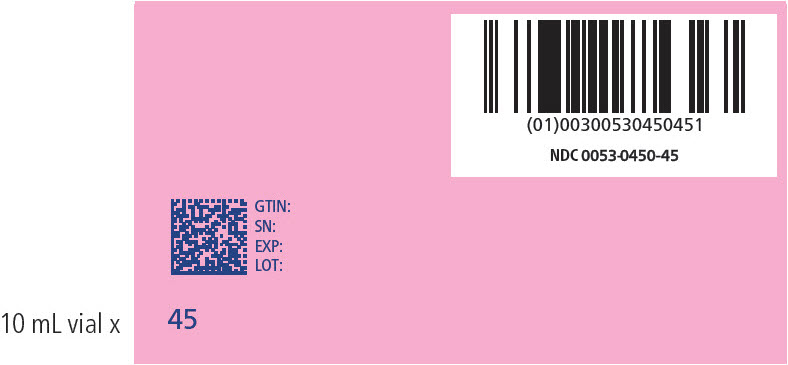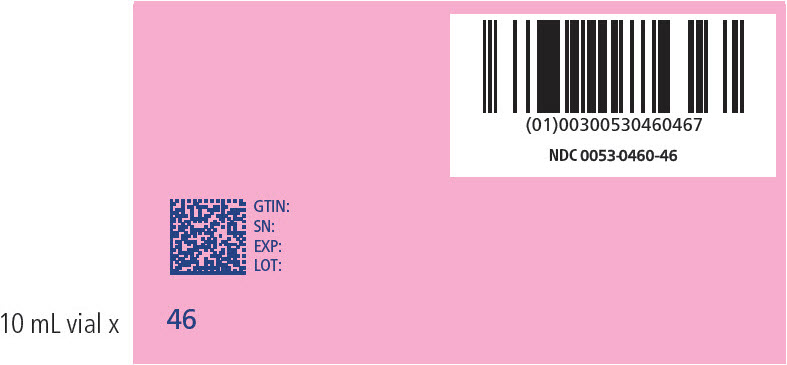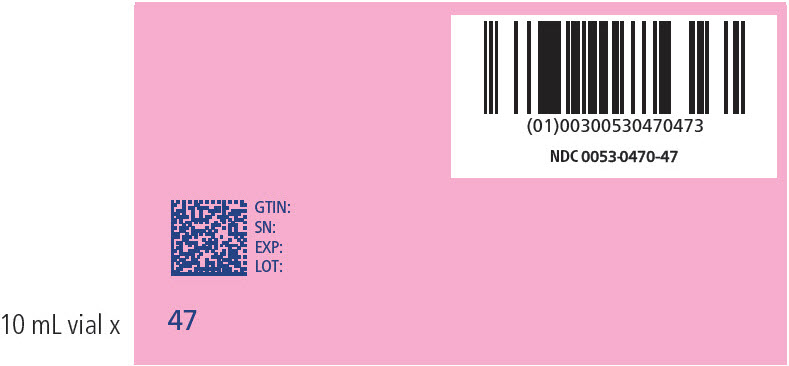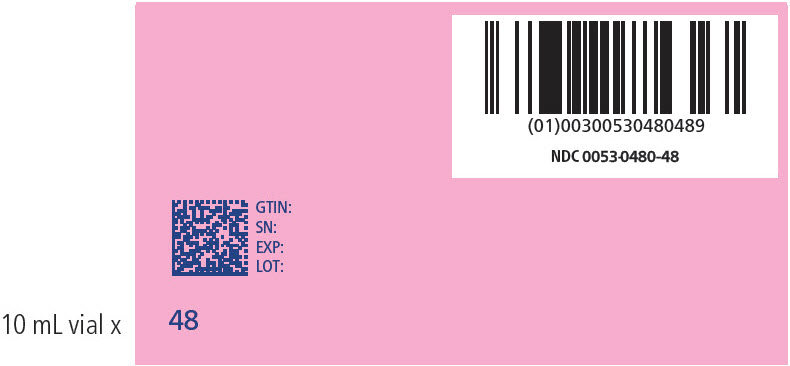 DRUG LABEL: HEMGENIX
NDC: 0053-0100 | Form: KIT | Route: INTRAVENOUS
Manufacturer: CSL Behring
Category: prescription | Type: HUMAN PRESCRIPTION DRUG LABEL
Date: 20250110

ACTIVE INGREDIENTS: etranacogene dezaparvovec 1013 {GC}/1 1

HIGHLIGHTS OF PRESCRIBING INFORMATION

These highlights do not include all the information needed to use HEMGENIX safely and effectively. See full prescribing information for HEMGENIX.
HEMGENIX (etranacogene dezaparvovec-drlb) suspension, for intravenous infusion
Initial U.S. Approval: 2022

1 INDICATIONS AND USAGE

HEMGENIX is an adeno-associated virus vector-based gene therapy indicated for the treatment of adults with Hemophilia B (congenital Factor IX deficiency) who:

- Currently use Factor IX prophylaxis therapy, or
- Have current or historical life-threatening hemorrhage, or
- Have repeated, serious spontaneous bleeding episodes.

2 DOSAGE AND ADMINISTRATION

For single-use intravenous infusion only. (2)

- Perform baseline testing to select patients, including testing for Factor IX inhibitor presence and liver health tests. (2.1)
- The recommended dose of HEMGENIX is 2 × 10^13 genome copies (gc) per kg of body weight. (2.1)
- Administer HEMGENIX as an intravenous infusion after dilution with 0.9% normal saline at a constant infusion rate of 500 ml/hour (8 mL/min). (2.1)

3 DOSAGE FORMS AND STRENGTHS

HEMGENIX is a suspension for intravenous infusion. (3)

HEMGENIX is provided in kits containing 10 to 48 single-use vials, each kit constituting a dosage unit based on the patient's body weight. (3)

HEMGENIX has a nominal concentration of 1 × 10^13 gc/mL, and each vial contains an extractable volume of not less than 10 mL (3)

4 CONTRAINDICATIONS

None. (4)

5 WARNINGS AND PRECAUTIONS

- Infusion reactions: Monitor during administration and for at least 3 hours after end of infusion. If symptoms occur, slow or interrupt administration. Re-start administration at a slower infusion once resolved. (2.3, 5.1)
- Hepatotoxicity: Closely monitor transaminase levels once per week for 3 months after HEMGENIX administration to mitigate the risk of potential hepatotoxicity. Continue to monitor transaminases in all patients who developed liver enzyme elevations until liver enzymes return to baseline. Consider corticosteroid treatment should elevations occur. (5.2)
- Hepatocellular carcinogenicity: For patients with preexisting risk factors (e.g., cirrhosis, advanced hepatic fibrosis, hepatitis B or C, non-alcoholic fatty liver disease (NAFLD), chronic alcohol consumption, non-alcoholic steatohepatitis (NASH), and advanced age), perform regular (e.g., annual) liver ultrasound and alpha-fetoprotein testing following administration. (5.4)
- Monitoring Laboratory tests: Monitor for Factor IX activity and Factor IX inhibitors. (5.5)

6 ADVERSE REACTIONS

The most common adverse reactions (incidence ≥5%) were elevated ALT, headache, blood creatine kinase elevations, flu-like symptoms, infusion-related reactions, fatigue, malaise and elevated AST. (6)

To report SUSPECTED ADVERSE REACTIONS, contact CSL Behring at 1-866-915-6958 or FDA at 1-800-FDA-1088 or www.fda.gov/medwatch.

8 USE IN SPECIFIC POPULATIONS

No dose adjustment is required in geriatric, hepatic, or renal impaired patients. (8.5, 8.6, 8.7)

FULL PRESCRIBING INFORMATION

1 INDICATIONS AND USAGE

HEMGENIX is an adeno-associated virus vector-based gene therapy indicated for treatment of adults with Hemophilia B (congenital Factor IX deficiency) who:

- Currently use Factor IX prophylaxis therapy, or
- Have current or historical life-threatening hemorrhage, or
- Have repeated, serious spontaneous bleeding episodes.

2 DOSAGE AND ADMINISTRATION

For single-use intravenous infusion only.

For patient selection:

- Perform Factor IX inhibitor titer testing.
  In case of a positive test result for human Factor IX inhibitors, perform a re-test within approximately 2 weeks. If both the initial test and re-test results are positive, do not administer HEMGENIX to this patient.
- Perform liver health assessments, including:
  - Enzyme testing [alanine aminotransferase (ALT), aspartate aminotransferase (AST), alkaline phosphatase (ALP) and total bilirubin)],
  - Hepatic ultrasound and elastography.
  In case of radiological liver abnormalities and/or sustained liver enzyme elevations, consider a consultation with hepatologist to assess eligibility for HEMGENIX [see Warnings and Precautions (5.2)].

2.1 Dose

The recommended dose of HEMGENIX is 2 × 10^13 genome copies (gc) per kilogram (kg) of body weight (or 2 mL/kg body weight) administered as an intravenous infusion after dilution with 0.9% sodium chloride solution (normal saline) [see Dosage and Administration (2.2)].
Calculate the dose as follows:

HEMGENIX dose (in mL) = patient body weight (in kilogram) × 2

The multiplication factor 2 represents the per kilogram dose (2 × 10^13 gc/kg) divided by the amount of genome copies per mL of the HEMGENIX solution (1 × 10^13 gc/mL).

Number of HEMGENIX vials needed = HEMGENIX dose (in mL) divided by 10 (round up to next whole number of vials).

The division factor 10 represents the extractable volume of HEMGENIX from each vial (10 mL).

The total volume of the patient's HEMGENIX dose to be diluted may be less than the total volume of vials needed.

Example calculation for 72 kg patient

Patient Weight | HEMGENIX dose (mL) (body weight multiplied by 2) | Number of Vials needed [HEMGENIX dose (mL) divided by 10, then rounded up]
72 kg | 144 mL | 15

HEMGENIX can be administered only once.

2.2 Preparation

The vials are for single-dose only.

General precautions

- Prepare HEMGENIX using sterile technique under aseptic conditions, proper engineering controls (e.g., biological safety cabinet or isolator) and according to institutional policies.
- Do not expose HEMGENIX to the light of an ultraviolet radiation disinfection lamp.
- Confirm that the patient's identity matches with the patient-specific identifier number on the outer carton.
- Verify the required dose of HEMGENIX based on the patient's body weight.
- Confirm that the carton contains sufficient number of vials to prepare the diluted HEMGENIX patient-specific infusion bag.
- Parenteral drug products should be inspected visually for particulate matter and discoloration prior to administration, whenever solution and container permit.

Required supplies and materials:

Normal saline infusion bag(s)* of 500 mL (1 to 2 bags based on patient's body weight)
Labels** for the infusion bag(s) of 500 mL
IV Infusion line/drip chamber* primed with 0.9% normal saline
Infusion bag connector(s)
20 mL or larger Luer-lock syringes*
20 G Needles* or vial adaptors*
70% isopropyl alcohol
Sharps disposal container

The following Table shows the supplies and materials compatible with HEMGENIX:

Component* | Material of Construction
Normal saline infusion bag (0.9% normal saline) | PE/PP copolymer (PVC-free) (Stability after dilution was established using PE/PP copolymer, PVC-free infusion bags with 0.9% normal saline.)
20 G Needle | Stainless Steel
Vial adapter | PP, Silicone; PP, stainless; MABS, acrylic silicone; ABS
Luer-lock syringe | PP, Silicone
IV Infusion line/drip chamber | PVC/TOTM, PP/styrene-ethylene-butylene-styrene
MABS = Methyl methacrylate acrylonitrile butadiene styrene; PE = Polyethylene; PP = Polypropylene; PVC = Polyvinyl chloride; TOTM = Trioctyltrimellitate, Acrylonitrile butadiene styrene (ABS)

**Information to be included on the infusion bag label:

- Product name: Diluted Hemgenix
- Patient identifier
- Expiration date/time (24 h from the vial removal from refrigerator)
- Storage condition: Room Temperature [15-25 °C (59-77 °F] protected from light.
- Contains genetically modified organisms
- Number of infusion bag: 1 of 2 bags / 2 of 2 bags

Preparation of 0.9% normal saline infusion bags

1. Prior to dilution, spike the infusion bag(s) of 0.9% normal saline solution with applicable connector.
2. Connect a luer-lock syringe at the mixing adapter site of the applicable connector.
3. Withdraw the volume equal to the calculated HEMGENIX dose (in mL) from the 500 mL infusion bag(s) of 0.9% normal saline solution. The volume to be withdrawn and number of infusion bag(s) needed will vary based on the patient body weight:

Patient body weight | Number of 500 mL 0.9% normal saline infusion bag(s) required | Volume of saline solution to withdraw
Less than 120 kg body weight | One | Equal to the total HEMGENIX dose (in mL) from one bag
Equal to or more than 120 kg body weight | Two | Equal to the total HEMGENIX dose (in mL). Remove half of the dose equivalent volume from each of the two bags.

HEMGENIX injection to the 0.9% normal saline infusion bags

  - Dilute HEMGENIX with 0.9% normal saline solution only prior to administration.
4. Prior to dilution, inspect each of the HEMGENIX single-dose vials.
  - If particulates, cloudiness, or discoloration is visible, DO NOT use the vial(s).
5. Gently swirl the vials 3 times (about 10 seconds) to homogenize the HEMGENIX suspension.
  - To avoid foaming, DO NOT shake the HEMGENIX vial(s).
6. Remove the plastic flip-off cap from the vials and disinfect the rubber stopper with a sterilizing agent (for example sterile 70% isopropyl alcohol).
7. Withdraw HEMGENIX from each vial using a 20 G needle/vial adapter and syringe.
  - Use recommended 20 mL luer-lock or larger syringe that is suitable for volume measuring and a needle.
  - DO NOT use filter needles during preparation of HEMGENIX.
  - Use a new needle/vial adapter and syringe for each HEMGENIX vial.
  - Dispose of the needle and syringe in an appropriate container.
8. Slowly add the required HEMGENIX dose from the syringe(s) directly to the 0.9% normal saline solution in the infusion bag(s) (from step #3) to bring the total volume in each infusion bag back to 500 mL.
  - DO NOT add HEMGENIX into the airspace of the bag to avoid foaming throughout this process.
9. Repeat steps 7 and 8 with additional needles/vial adaptors and syringes to inject the total calculated HEMGENIX volume to the infusion bag(s) required for the patient dose.
10. Gently invert the infusion bag(s) at least 3 times (about 10 seconds) to mix the solution and ensure even distribution of the diluted product.
  - To avoid foaming, DO NOT shake the diluted HEMGENIX infusion bag(s).
11. Label the infusion bag(s).
12. Connect the infusion bag(s) to an infusion tube pre-filled with sterile 0.9% normal saline solution to reduce the risk of spillage and/or aerosol formation.
13. Transport the diluted HEMGENIX infusion bag(s) in the transport container/bag protected from light to the administration site, avoiding any shaking or excessive agitation.

2.3 Administration

Required supplies and materials for administration:

Winged intravenous needle or catheter set*
Infusion pump
0.2 mcm in-line filter*
Antiseptic skin preps
70% isopropyl alcohol wipes
Gauze and tape, or transparent dressing
Sharps disposal container
Virucidal agent to treat spill/spill kit

The following Table shows the supplies and materials compatible for infusion of HEMGENIX:

Component* | Material of Construction
Winged IV needle or catheter set | PVC/TOTM, MABS
0.2 mcm in-line filter | PES
Catheter | PVC/DEHT, Stainless steel
DEHP = Di(2-ethylhexyl)phthalate; DEHT = Di(2-ethylhexyl)terephthalate; MABS = Methyl methacrylate acrylonitrile butadiene styrene; PES = Polyether sulfone; PVC = Polyvinyl chloride

Administer HEMGENIX as a single-dose intravenous infusion through a peripheral venous catheter:

1. Visually inspect diluted HEMGENIX prior to administration. The diluted HEMGENIX should be clear and colorless.
  - DO NOT use if particulates, cloudiness, or discoloration are visible.
  - Use the diluted HEMGENIX within 24 hours after the dose preparation [see How supplied/Storage and Handling (16.2)].
2. Use an integrated (in-line) 0.2 mcm filter made out of PES.
3. Subsequently, connect the pre-filled IV infusion line/drip chamber to the main intravenous line which has been primed with sterile 0.9% normal saline solution prior to use.
4. Infuse diluted HEMGENIX at a constant infusion rate of 500 mL/hour (8 mL/min).
  - DO NOT administer HEMGENIX as an intravenous push or bolus.
  - DO NOT infuse the diluted HEMGENIX solution in the same intravenous line with any other products.
  - DO NOT use a central line or port.
  In the event of an infusion reaction during administration [see Warnings and Precautions (5.1)]:
  - The rate of infusion may be reduced or stopped, to manage the infusion reaction.
    If the infusion is stopped, restart at a slower rate when the infusion reaction is resolved.
  - If the infusion rate needs to be reduced, or stopped and restarted, HEMGENIX should be infused within 24 hours after the dose preparation [see How supplied/Storage and handling (16.2)].
5. After the entire content of the bag(s) is infused, flush the IV infusion line/drip chamber at the same infusion rate with 0.9% normal saline solution to ensure all HEMGENIX is delivered.
  - Treat spills of HEMGENIX with a virucidal agent with proven activity against non-enveloped viruses.
  - Dispose of unused product and disposable materials that may have come in contact with HEMGENIX in accordance with local biosafety guidelines applicable for handling and disposal of the pharmaceutical waste.

Monitoring Post-Administration

Conduct the following tests after HEMGENIX administration [see Warnings and Precautions (5.2, 5.3, 5.4)]:

- Perform regular liver enzyme testing to monitor for liver enzyme elevations which may indicate immune-mediated hepatotoxicity:
  - Monitor ALT and AST (transaminase) levels by testing weekly for 3 months following administration of HEMGENIX. Continue to monitor transaminases in all patients who developed liver enzyme elevations until liver enzymes return to baseline.
  - In the event of ALT increase to above normal limits or to twice the patient`s baseline in the first 3 months post-dose, consider implementing a course of corticosteroids. For patients with clinically relevant ALT increases who need corticosteroid treatment, administer the recommended starting dose of 60 mg/day of oral prednisolone or prednisone, with a subsequent taper in response to normalization of the ALT levels (see Table 1):
  Table 1. Prednisolone Treatment Applied in Clinical Studies With HEMGENIX:
  Timeline | [Medications equivalent to prednisolone may also be used. A combined immunosuppressant regimen or the use of other products can be considered in case of prednisolone treatment failure or contraindication.] Prednisolone Oral Dose (mg/day)
  Week 1 | 60
  Week 2 | 40
  Week 3 | 30
  Week 4 | 30
  Maintenance dose until ALT level returns to baseline level | 20
  Taper dose after ALT baseline level has been reached | Reduce daily dose by 5 mg/week
  In the clinical studies, the mean duration of corticosteroid use for elevated transaminases was 81.4 days [Standard Deviation (SD) 28.6] and ranged from 51 to 130 days [see Warnings and Precautions (5.2)].
- Monitor Factor IX activity (e.g., weekly for 3 months).
  - Monitor patients regularly for their Factor IX activity, in particular when exogenous Factor IX is administered. It may take several weeks before improved hemostatic control becomes apparent after HEMGENIX infusion; therefore, continued hemostatic support with exogenous human Factor IX may be needed during the first weeks after HEMGENIX infusion [see Clinical Pharmacology (12.3)].
  - The use of different assays may impact the test results; therefore, use the same assay and reagents to monitor patients over time, if feasible [see Monitoring Laboratory Tests (5.5)].
  - Use of exogenous Factor IX concentrates before and after HEMGENIX administration may impede assessment of endogenous, HEMGENIX-derived Factor IX activity.
- Perform regular alpha-fetoprotein (AFP) level testing and abdominal ultrasound (e.g., annually) in patients with preexisting risk factors for hepatocellular carcinoma (e.g., in patients with cirrhosis, advanced hepatic fibrosis, hepatitis B or C, non-alcoholic fatty liver disease (NAFLD), chronic alcohol consumption, non-alcoholic steatohepatitis (NASH), and advanced age).
- Monitor patients for human Factor IX inhibitors. Post-dose inhibitor testing should be performed if bleeding is not controlled, or plasma Factor IX activity levels decrease [see Warnings and Precautions (5.5)].

3 DOSAGE FORMS AND STRENGTHS

HEMGENIX is a clear and colorless suspension for intravenous infusion.

HEMGENIX is provided in a kit containing 10 to 48 vials. Each kit constitutes a dosage unit based on the patient's body weight.

HEMGENIX has a nominal concentration of 1 × 10^13 gc/mL, and each vial contains an extractable volume of not less than 10 mL.

4 CONTRAINDICATIONS

None.

5 WARNINGS AND PRECAUTIONS

5.1 Infusion Reactions

Infusion reactions, including hypersensitivity reactions and anaphylaxis, may occur. Symptoms may include chest tightness, headaches, abdominal pain, lightheadedness, flu-like symptoms, shivering, flushing, rash, and hypertension. Closely monitor patients for signs or symptoms of an infusion reaction throughout the infusion period and for at least 3 hours after end of infusion. Do not infuse the product faster than 500 mL/hour [see Adverse Reactions (6)].

In the event of an infusion reaction during administration, the infusion may be slowed or stopped. If the infusion is stopped, restart at a slower rate when the infusion reaction has resolved. Consider treatment with a corticosteroid or antihistamine for management of an infusion reaction [see Dosage and Administration (2.1)].

5.2 Hepatotoxicity

Intravenous administration of a liver-directed AAV vector could potentially lead to liver transaminase elevations (transaminitis). Transaminitis, particularly when observed in the first 3 months after HEMGENIX administration, is presumed to occur due to immune-mediated injury of transduced hepatocytes and may reduce the therapeutic efficacy of the AAV-vector based gene therapy.

In clinical studies with HEMGENIX, most subjects had asymptomatic, and predominantly mild elevations in transaminases. Elevated ALT levels occurred most often in the first 4 months after HEMGENIX administration. There were some subjects who had a late onset of elevated ALT levels between Months 6-24 (range = 42 IU/L-193 IU/L); however, all of these ALT values were <2× ULN with the exception of one subject. Three additional subjects had AST elevations with onset and resolution between Months 6 and 12 (range = 41 IU/L – 96 IU/L).

In one subject, an ALT elevation >5× ULN occurred 24 days after HEMGENIX administration and resolved by 51 days post-HEMGENIX administration. There was one subject who had an AST elevation > 5× ULN that occurred 11 months post-HEMGENIX administration and resolved to <2× ULN eight days later.

The majority of the elevated ALT values returned to baseline, however 9 subjects' ALT values never resolved to normal (range at 2-year follow up = 48 IU/L – 193 IU/L) [see Adverse Reactions (6)].

Closely monitor transaminase levels once per week for 3 months after HEMGENIX administration to mitigate the risk of potential hepatotoxicity. Continue to monitor transaminases in all patients who developed liver enzyme elevations until liver enzymes return to baseline [see Dosage and Administration (2.3)].

In case of increased ALT levels above the upper limit of normal or double baseline levels, consider implementing a course of corticosteroid, along with human Factor IX activity monitoring [see Dosage and Administration (2.3)].

5.3 Immune-mediated neutralization of the AAV5 vector capsid

In AAV-vector based gene therapies, preexisting neutralizing anti-AAV antibodies may impede transgene expression at desired therapeutic levels. Following treatment with HEMGENIX all subjects developed neutralizing anti-AAV antibodies. Currently, there is no validated neutralizing anti-AAV5 antibody assay.

In the clinical studies with HEMGENIX, an unvalidated clinical trial assay was utilized to assess preexisting neutralizing anti-AAV5 antibodies. The subject sub-group with detectable preexisting neutralizing anti-AAV5 antibodies up to titers of 1:678 showed mean Factor IX activity that was numerically lower compared to that subject sub-group without detectable preexisting neutralizing anti-AAV5 antibodies. Subjects, with and without preexisting neutralizing anti-AAV5 antibodies, demonstrated hemostatic protection. In one subject with a preexisting neutralizing anti-AAV5 antibody titer of 1:3212, no human Factor IX expression was observed, and restart of the exogenous Factor IX prophylaxis was needed for bleeding events. [see Clinical Studies (14)].

Anti-AAV5 Antibody Study

Patients who intend to receive treatment with HEMGENIX are encouraged to enroll in a study to measure pre-existing anti-AAV5 neutralizing antibodies by calling CSL Behring at 1-800-504-5434. The study evaluates the effect of pre-existing anti-AAV5 neutralizing antibodies on the risk of bleeding.

5.4 Hepatocellular carcinogenicity

The integration of liver-targeting AAV vector DNA into the genome may carry the theoretical risk of hepatocellular carcinoma development.

HEMGENIX is composed of a non-replicating AAV5 vector whose DNA persists largely in episomal form. Random integration of HEMGENIX vector DNA to the human DNA at low frequency is possible. No HEMGENIX-associated clonal expansion or carcinogenicity was observed in clinical studies [see Clinical Studies (14)]. One subject with preexisting risk factors for developing hepatic cancer developed a hepatocellular carcinoma, which was assessed as not likely related to HEMGENIX treatment based on vector integration site analyses and whole genome sequencing.

Patients with preexisting risk factors for hepatocellular carcinoma (e.g., patients with cirrhosis, advanced hepatic fibrosis, hepatitis C or B, non-alcoholic fatty liver disease (NAFLD), chronic alcohol consumption, non-alcoholic steatohepatitis (NASH), and advanced age) should receive abdominal ultrasound screenings and be monitored regularly (e.g., annually) for alpha-fetoprotein (AFP) elevations in the 5 years following administration [see Dosage and Administration (2.3)].

5.5 Monitoring Laboratory Tests

After HEMGENIX administration, regularly monitor patient's Factor IX activity levels.

When using an in vitro activated partial thromboplastin time (aPTT)-based one-stage clotting assay (OSA) for determining Factor IX activity, plasma Factor IX activity results can be affected by both the type of aPTT reagent and the reference standard used in the assay. This is important to consider particularly when changing the laboratory and/or reagents used in the assay. Therefore, the same assay and reagents are recommended to be used to monitor Factor IX activity over time.

The results of Factor IX activity tests are lower if measured with chromogenic substrate assay (CSA) compared to OSA.

In the clinical efficacy study with HEMGENIX, the post-dose Factor IX activity measured with CSA returned lower values with the mean CSA to OSA Factor IX activity ratio ranging from 0.41 to 0.55.

Monitor patients through appropriate clinical observations and laboratory tests for the development of inhibitors to Factor IX after HEMGENIX administration. Perform an assay that detects Factor IX inhibitors if bleeding is not controlled, or plasma Factor IX activity levels decrease.

6 ADVERSE REACTIONS

The most common adverse reactions (incidence ≥5%) reported in clinical studies were ALT elevations, headache, blood creatine kinase elevations, flu-like symptoms, infusion-related reactions, fatigue, malaise, and AST elevations.

The following adverse reactions are discussed in greater detail in other sections of the label:

- Infusion related reactions [see Warnings and Precautions (5.1)].
- Hepatotoxicity [see Warnings and Precautions (5.2)].
- Immune-mediated neutralization of the AAV5 vector capsid [see Warnings and Precautions (5.3)].

6.1 Clinical Trials Experience

Because clinical trials are conducted under widely varying conditions, adverse reaction rates observed in the clinical trials of a drug cannot be directly compared to rates in the clinical trials of another drug and may not reflect the rates observed in clinical practice.

The safety of HEMGENIX was evaluated in two clinical studies (the first study enrolled 3 subjects and the second study 54 subjects). Both studies enrolled adult male subjects with moderately severe or severe Hemophilia B (N = 57), who received a single intravenous dose of 2 × 10^13 gc/kg body weight of HEMGENIX. All subjects entered a follow-up period of 5 years.

No serious adverse reactions were reported [see Clinical Studies (14)]. The most common adverse reactions observed in ≥5% of subjects post-dose are listed in Table 2:

Table 2. Adverse Reactions (Incidence ≥5%) Following Treatment with HEMGENIX
Adverse Reactions ≥5% | Subjects (%) (N = 57)
Alanine aminotransferase increased | 24 (42%)
Headache | 10 (18%)
Blood creatine kinase increased | 24 (42%)
Flu-like symptoms | 8 (14%)
Infusion-related reactions [Infusion-related reaction: In 7 subjects symptoms occurred during infusion, in 12 subjects after infusion. Symptoms occurring in ≥ 5% of subjects were: Dizziness, Flu-like symptoms and Headache. Symptoms occurring in < 5% of subjects were: Abdominal pain, Abdominal discomfort, Chest discomfort, Chills, Eye pruritus, Fever (Pyrexia), Flushing, Hives (Urticaria), Infusion site reaction, and Tachycardia. Eleven subjects recovered on the day or day one after infusion. Eight subjects recovered within 8 days after infusion.] (see below) | 19 (33%)
Hypersensitivity | 2 [1of 2 hypersensitivity reactions – 12 minutes after initiation of administration of HEMGENIX, the patient experienced high blood pressure, red eyes, feeling warm, dizziness, coughing, dyspnea, elevated heart rate, shivering, and leg cramps. Infusion was stopped and not restarted. Only 10% of the HEMGENIX dose was administered. The patient recovered on the same day after treatment with intravenous diphenhydramine and intramuscular epinephrine. 2 of 2 hypersensitivity reactions – 10 minutes after initiation of administration of HEMGENIX, the patient experienced itching, tightness of throat, and swelling of the right side of the neck. The HEMGENIX dose was not interrupted and administered in full. All symptoms resolved on the same day without treatment.] (4%)
Fatigue | 7 (12%)
Aspartate aminotransferase increased | 24 (42%)
Nausea | 4 (7%)
Malaise | 7 (12%)

Infusion-related reactions were observed in 19 subjects. Infusions were temporarily interrupted in 3 subjects and resumed at a slower infusion rate after treatment with antihistamines and/or corticosteroids. In one subject, infusion was stopped and not resumed (see footnote of Table 2).

There were 24 subjects who had elevated ALT values from Day 8 to 731 post-administration.

Five subjects had ALT elevations >2-3× ULN (range = 89 IU/L – 130 IU/L), one subject had an ALT elevation > 3-5× ULN (193 IU/L) and one subject had an ALT elevation > 5× ULN (275 IU/L). The subject who had the ALT elevation >5× ULN occurred 3 weeks after HEMGENIX administration.

Five subjects had AST elevations > 2-3× ULN (range = 71 IU/L – 118 IU/L), three subjects had AST elevations > 3-5× ULN (range = 127 IU/L – 163 IU/L) and one subject had an AST elevation > 5× ULN (327 IU/L). The subject who had the AST elevation > 5× ULN occurred 11 months post-HEMGENIX administration.

Seventeen subjects had elevations in ALT levels within the first 4 months after HEMGENIX infusion (range = 41 IU/L – 275 IU/L), eleven of these subjects' ALT levels resolved within 4 months post-infusion (range = 41 IU/L – 275 IU/L) and five of these subjects' ALT levels never normalized as of last follow-up (range of values at 2-year follow-up = 48 IU/L – 110 IU/L). Seven additional subjects had ALT elevations with onset between Months 6 to 24 (range = 42 IU/L-193 IU/L), five of these subjects had additional risk factors for having elevated transaminase levels including Hepatitis C and Human Immunodeficiency Virus (HIV). ALT levels never normalized as of last follow-up (range of values at 2-year follow-up = (59 IU/L- 193 IU/L) in three of the subjects with ALT elevations with onset between Months 6 to 24.

Nineteen subjects had elevations in AST levels within 3 months after HEMGENIX infusion (range = 32 IU/L- 163 IU/L). Nine of these subjects' AST elevations resolved within 4 months post-infusion (range = 35 IU/L – 163 IU/L), three resolved within 7 to 13 months post-infusion (range = 35 IU/L – 62 IU/L), and seven of these subjects' AST levels never normalized as of last follow-up (range of values at 2-year follow-up = 36 IU/L – 327 IU/L). The remaining 5 subjects with AST elevation had onset of between 6 months and 2 years post-infusion (range = 36 IU/L – 127 IU/L), and AST levels had not normalized as of the last follow-up for one subject (AST at 2-year follow-up = 127 IU/L) who had additional risk factors for having elevated transaminase levels.

Nine subjects with ALT elevations received a tapered course of corticosteroids. The mean duration of corticosteroid treatment for the elevated ALT was 81.4 days. Nineteen of the 24 subjects with ALT elevations also had a related AST elevation. Twenty-one subjects had elevated transaminase levels and were not treated with corticosteroids. [see Clinical Studies (14)].

8 USE IN SPECIFIC POPULATIONS

8.1 Pregnancy

Risk Summary

HEMGENIX is not intended for administration in women. No adverse effects on mating rate and fertility indices or fetal weights were observed in healthy naïve female mice mated with healthy male mice that were intravenously administered a predecessor of HEMGENIX product 6 days prior to mating. Vector DNA was not detected in the uterus, placenta, or fetus.

In the United States general population, the estimated background risk of major birth defects and miscarriage in clinically recognized pregnancies is 2 to 4% and 15 to 20%, respectively.

8.2 Lactation

Risk Summary

HEMGENIX is not intended for administration in women.

8.3 Females and Males of Reproductive Potential

Risk Summary

No clinical studies have been performed to evaluate the effects of HEMGENIX on fertility in humans. Twenty days after intravenous administration of a predecessor of HEMGENIX product in healthy male mice, vector DNA was detected in all reproductive tissues examined (epididymis, seminal vesicles, testes, and sperm). However, no differences were observed in mating rates and fertility indices in healthy naïve female mice following mating with the dosed males.

8.4 Pediatric Use

The safety and efficacy of HEMGENIX in pediatric patients have not been established.

8.5 Geriatric Use

The clinical studies included a total of 6 geriatric subjects with Hemophilia B, aged 68 to 75 years at time of enrollment. No meaningful differences in the safety and efficacy profile were observed in these subjects compared to subjects aged 18 to 65 years, and no dose adjustment was made [see Clinical Studies (14)].

8.6 Hepatic Impairment

Limited clinical data in subjects with liver impairment indicate numerically lower FIX activity as compared to subjects without hepatic impairment [see Clinical Pharmacology (12.3)]. In the clinical studies, no dose adjustment was made in subjects with hepatic pathologies. The safety and efficacy in subjects with advanced hepatic impairment, including cirrhosis, advanced liver fibrosis, or uncontrolled Hepatitis B and C, have not been studied.

8.7 Renal Impairment

Limited clinical data are available in subjects with mild and moderate renal impairment [see Clinical Pharmacology (12.3)]. In the clinical studies, no dose adjustment was made in these subjects. The safety and efficacy in subjects with severe renal impairment and end-stage renal disease have not been studied.

11 DESCRIPTION

HEMGENIX (etranacogene dezaparvovec-drlb) is an adeno-associated viral vector-based gene therapy for intravenous infusion after dilution. HEMGENIX is a non-replicating recombinant AAV5 containing a codon-optimized DNA sequence of the gain-of-function Padua variant of human Factor IX (variant R338L), under control of a liver-specific promotor 1 (LP1).

HEMGENIX has a nominal concentration of 1 × 10^13 gc/mL. Each vial contains an extractable volume of no less than 10 mL of HEMGENIX and the following excipients: sucrose (50 mg/mL), polysorbate-20 (0.22 mg/mL), potassium chloride (0.2 mg/mL), potassium phosphate (0.2 mg/mL), sodium chloride (8 mg/mL), and sodium phosphate (1.2 mg/mL).

HEMGENIX is sterile, clear and colorless suspension, and contains no preservative. After dilution, HEMGENIX should be clear and colorless suspension.

12 CLINICAL PHARMACOLOGY

12.1 Mechanism of Action

HEMGENIX is an adeno-associated virus serotype 5 (AAV5) based gene therapy designed to deliver a copy of a gene encoding the Padua variant of human coagulation Factor IX (hFIX-Padua). Single intravenous infusion of HEMGENIX results in cell transduction and increase in circulating Factor IX activity in patients with Hemophilia B.

12.2 Pharmacodynamics

Factor IX activity

The mean Factor IX activity levels over time, as measured by one-stage [activated Partial Thromboplastin Time (aPTT)-based] assay are summarized in Table 3. Subjects achieved a mean (± SD) uncontaminated (i.e., excluding measurements within five half-lives of Factor IX replacement therapy) Factor IX activity levels of 39% (± 18.7), 41.5% (± 21.7), 36.9% (± 21.4) and 36.7 (± 19.0) of normal, respectively, at 6, 12, 18 and 24 months. The time to onset of Factor IX protein expression post-dose was detectable by first uncontaminated measurement at Week 3 in the clinical efficacy study (N = 54) [see Clinical Studies (14)].

Table 3: Summary of Uncontaminated Factor IX Activity Over Time Following Administration of 2 × 10^13 gc/kg of HEMGENIX [FAS; One-Stage (aPTT-Based) Assay]
 | Factor IX Activity in % (One-stage)
 | Subject Number ([Contaminated and missing values are not shown here. Specifically, the number of subjects excluded for contamination with Factor IX replacement therapy at Week 3, Month 3, Month 6, Month 12, Month 18, and Month 24, were 10, 3, 3, 3, 3, 2, respectively] n) | Median (Min, Max) | Mean (SD)
Week 3 | 43 | 23.7 (4.9, 56.7) | 26.8 (12.7)
Month 3 | 51 | 33.8 (7.6, 91.0) | 36.8 (18.2)
Month 6 | 51 | 37.3 (8.2, 97.1) | 39.0 (18.7)
Month 12 | 50 | 39.9 (5.9, 113.0) | 41.5 (21.7)
Month 18 | 50 | 33.6 (4.5, 122.9) | 36.9 (21.4)
Month 24 | 50 | 33.9 (4.7, 99.2) | 36.7 (19.0)
Abbreviations: SD = Standard Deviation; FAS = Full Analysis Set including all 54 subjects dosed; Min = Minimum; Max = Maximum. Uncontaminated Factor IX activity values exclude measurements within five half-lives of Factor IX replacement therapy.

Pharmacodynamics in specific populations

Age

Limited data (N = 7) from 60 -75 years subgroup showed that the mean Factor IX activity levels were approximately up to 2-fold higher in this subgroup compared to 18 to < 40 years age subgroup (N = 31), but comparable to 40 to <60 years age subgroup (N = 15).

Hepatic Impairment

In the clinical efficacy study, subjects with varying degree of baseline liver pathology, specifically the degree of hepatic steatosis with the Controlled Attenuation Parameter (CAP) score of ≥S2 (≥260 decibels/m; range: 262 to 400; n = 12) versus <S2 (<260 decibels/m; range: 100 to 259; n = 28;) and missing score (n = 14) were compared [see Clinical Studies (14)]. The mean (± SD) uncontaminated Factor IX activity for <S2 versus ≥S2 subgroups at Months 6, 12, 18, and 24 post dose were 40.8 (±20.1) versus 34.5 (±13.7), 46.4 (±24.1) versus 32.6 (±18.6), 41.6 (±25.7) versus 29.2 (±13.7), and 40.2 (±19.8) versus 28.4 (±13.1), respectively.

Subjects with advanced liver impairment and advanced fibrosis (elastography of e.g., ≥9 kPA, or suggestive of or equal to METAVIR Stage 3 disease), were not studied.

Renal Impairment

In the clinical efficacy study, subjects with mild renal impairment (creatinine clearance (CLcr) = 60 to 89 mL/min defined by Cockcroft-Gault equation, n = 7) had about 37% higher Factor IX activity relative to those with normal renal function (CLcr ≥90 mL/min; n = 45) following HEMGENIX administration. One subject with moderate renal impairment (CLcr = 30 to 59 mL/min) had similar Factor IX activity as subjects with normal renal function.

HEMGENIX was not studied in subjects with severe renal impairment (CLcr = 15 to 29 mL/min) or end-stage renal disease (CLcr< 15 mL/min).

12.3 Pharmacokinetics

Vector Biodistribution (within the body) and Vector Shedding (excretion/secretion)

Nonclinical data

Biodistribution of HEMGENIX was evaluated after intravenous administration in healthy male mice and non-human primates (NHPs). The highest levels of vector DNA were detected in the liver and adrenal glands in both species. Vector DNA was also detected in all reproductive tissues examined (epididymis, seminal vesicles, and testes). In a mating study evaluating a predecessor of HEMGENIX, transmission of vector DNA to naïve female mice following mating with dosed males was not observed [see Nonclinical Toxicology (13.2)].

Clinical data

Following administration of the predecessor of HEMGENIX at doses of 5 ×10^12 (N = 5) and 2 × 10^13 gc/kg (N = 5) in a clinical study, the pharmacokinetics of vector DNA in blood and viral shedding in saliva, nasal secretions, semen, urine, and feces were characterized. Clearance of vector DNA as confirmed by 3 subsequent measurements below limit of detection (LOD), was achieved in all subjects at both dose levels from all the matrices except for semen, where clearance was achieved in 9/10 subjects. One subject was unable to produce semen due to a historical medical condition and, therefore, shedding from semen could not be assessed. The maximum time to clearance of vector DNA was 22 weeks for urine, 26 weeks for saliva and nasal secretions, 40 weeks for feces, 52 weeks for semen, and 159 weeks for blood.

Subsequently, the pharmacokinetics of vector DNA in blood, and viral shedding in semen following HEMGENIX administration was characterized in 2 clinical studies.

In an initial clinical study (N = 3), clearance of vector DNA from semen and blood (i.e., confirmed with 3 subsequent measurements below LOD of vector DNA) was achieved in 2/3 subjects, and in all subjects, respectively, after 3 years post-administration. One subject did not return the required number of semen samples to assess the shedding status as per the definition of 3 subsequent measurements below LOD of vector DNA.

In the clinical efficacy study (N = 54), a total of 56% (30/54) of subjects achieved absence of vector DNA from blood and 69% (37/54) from semen by Month 24. Several subjects did not return the required number of blood and semen samples to assess the shedding status as per the definition of 3 subsequent measurements below LOD of vector DNA. Considering results obtained from 2 available consecutive samples below LOD, a total of 40/54 (74%) and 47/54 (87%) subjects were identified to have reached absence of vector DNA from blood and semen, respectively, at 24 months post-administration.

12.6 Immunogenicity

In clinical studies sustained humoral immune response to infused AAV5 capsid was observed in all subjects following treatment with HEMGENIX. The neutralizing anti-AAV5 antibody levels raised above the upper limit of quantification by week 3 post-administration and remained elevated, as measured at month 24 post-dose. Re-administration of HEMGENIX in the presence of high anti-AAV5 antibody titer has not been evaluated. Currently, there is no validated neutralizing anti-AAV5 antibody assay.

13 NONCLINICAL TOXICOLOGY

Nonclinical studies were initiated with a predecessor of HEMGENIX product, rAAV5 expressing the wild type human coagulation factor IX (rAAV5-hFIX). HEMGENIX was developed by introducing a 2-nucleotide change in the transgene for hFIX, generating the naturally occurring Padua variant of Factor IX (rAAV5-hFIX-Padua).

13.1 Carcinogenesis, Mutagenesis, Impairment of Fertility

No traditional nonclinical carcinogenicity or mutagenicity studies were conducted with HEMGENIX; such studies were not indicated. No adverse effects were observed in mating rates and fertility indices in healthy naïve female mice following mating with males that were administered the predecessor of HEMGENIX [see Use in specific populations (8.3)]. To evaluate vector integration, host genomic DNA was isolated from liver tissue obtained from healthy mice and NHPs following intravenous administration of the predecessor of HEMGENIX. For both species, the identified rAAV5-hFIX vector DNA sequences represented episomal forms that were not integrated into the host DNA. A low level of integrated rAAV5-hFIX DNA was distributed throughout the host genome with no predilection to specific integration sites, including in genes associated with malignant transformation in humans.

13.2 Animal Toxicology and/or Pharmacology

A pharmacology study was conducted in a murine model of Hemophilia B (B6.129P2-F9tm1Dws. Intravenous administration of the predecessor of HEMGENIX at dose levels ranging from 5×10^11 to 2.3×10^14 gc/kg, resulted in dose-dependent increases in plasma hFIX protein levels, plasma hFIX clotting activity, and vector transduction in the liver at 4 weeks post-dose.

Intravenous administration of HEMGENIX resulted in a no-observed-adverse-effect-level of 5 × 10^13 gc/kg (the maximum dose level administered) in healthy mice and 9 × 10^13 gc/kg in NHPs. Vector biodistribution to the liver and hFIX protein levels in the plasma occurred in a dose-dependent manner in both species. Anti-hFIX antibodies developed in 5 out of 12 NHPs administered HEMGENIX, which correlated with a decline in circulating hFIX protein levels beginning at 13 weeks post-dose.

One out of 10 healthy mice administered 5 × 10^13 gc/kg of HEMGENIX or the predecessor of HEMGENIX developed pulmonary thrombi at 13 weeks post-dose. This dose level is 2.5-fold higher than the recommended dose level for HEMGENIX. Compared to concurrent controls, prolonged prothrombin time, decreased activated partial thromboplastin time and decreased heart rates were observed in NHPs administered 9 × 10^13 gc/kg of HEMGENIX during the 26-week study. This dose level is 4.5-fold higher than the recommended dose level for HEMGENIX.

14 CLINICAL STUDIES

The efficacy of HEMGENIX was evaluated in a prospective, open-label, single-dose, single-arm, multi-national study (N = 54). The study enrolled adult male subjects aged 19 to 75 years, with severe or moderately severe Hemophilia B, who received a single intravenous dose of 2 × 10^13 gc/kg body weight of HEMGENIX and entered a follow-up period of 5 years. The study is on-going.

The 54 subjects prospectively completed a lead-in period of at least six months with the intent to receive standard of care routine Factor IX prophylaxis. These 54 subjects then received the indicated single intravenous dose of HEMGENIX. Subjects were then followed up monthly until Month 12, and then at 6-month intervals until Year 5. For the efficacy evaluation, data up to 18 months post-treatment were used. Of the 54 subjects, 53 subjects completed at least 18 months of follow-up in the ongoing study. One subject with numerous cardiovascular and urologic risk factors, aged 75 years at screening, died of urosepsis and cardiogenic shock at Month 15 post-dose (at age 77 years) unrelated to treatment. Another subject received around 10% of the intended dose of HEMGENIX due to an infusion-related hypersensitivity reaction.

The main efficacy outcome was a non-inferiority test of annualized bleeding rate (ABR) during Months 7 to 18 after HEMGENIX treatment compared with ABR during the lead-in period. All bleeding episodes, regardless of investigator assessment, were counted. Subjects were allowed to continue prophylaxis during Months 0 to 6. The estimated mean ABR during Months 7 to 18 after HEMGENIX treatment was 1.9 bleeds/year with a 95% confidence interval (CI) of (1.0, 3.4), compared with an estimated mean ABR of 4.1 [95% CI: 3.2, 5.4] during the lead-in period. The ABR ratio (Months 7 to 18 post-treatment / lead-in) was 0.46 [95% CI: 0.26, 0.81], demonstrating non-inferiority of ABR during Months 7 to 18 compared to the lead-in period.

Two subjects were not able to stop routine prophylaxis after HEMGENIX treatment. During Months 7 to 18, an additional subject received prophylaxis from Days 396-534 [approximately 20 weeks].

Table 4. Total Bleeding Events and ABRs (Full Analysis Set: N=54)
 | Lead-in Period [During the observational lead-in period subjects used their individualized approach to Factor IX prophylaxis derived prior to enrollment in the study, rather than a standardized approach to Factor IX prophylaxis. Not all subjects complied with their prescribed prophylaxis regimen during the lead-in period.] | Months 7 to 18 [Efficacy evaluation started from Month 7 after HEMGENIX treatment, to allow Factor IX expression to reach a steady state.] after HEMGENIX treatment
All Bleeds | 136 | 96 [An ABR of 20 was imputed for the period when three subjects were on continuous prophylaxis.]
Follow-up time (Person-Year) | 33 | 52
Mean Adjusted ABR (95% CI) [Non-inferiority comparison and mean ABR estimates were based on a repeated measures generalized estimating equations negative binomial regression model.] | 4.1 (3.2, 5.4) | 1.9 (1.0, 3.4)
Subjects with Bleeds | 40 (74%) | 20 (37%)
Subjects with Zero Bleeds | 14 (26%) | 34 (63%)
Observed Spontaneous Bleed Count (Proportion of total bleeds) [For spontaneous and joint bleed counts, no imputation was done for the three subjects receiving continuous prophylaxis during Months 7 to 18.] | 50 (37%) | 14 (26%)
Observed Joint Bleed Count (Proportion of total bleeds) | 77 (57%) | 19 (35%)
Abbreviations: ABR = Annualized Bleeding Rate; CI = Confidence Interval

After a single-dose of HEMGENIX, increases in Factor IX activity were observed [see Pharmacokinetics (12.3)].

16 HOW SUPPLIED/STORAGE AND HANDLING

16.1 How Supplied

HEMGENIX is supplied as sterile, preservative-free, clear, and colorless suspension. HEMGENIX has a nominal concentration of 1 × 10^13 gc/mL.

HEMGENIX is provided as a customized kit to meet dosing requirements for each patient [see Dosage and Administration (2.1)], with each kit containing 10 (ten) to 48 (forty-eight) single-use vials (NDC 0053-0099-01), each with an extractable volume of no less than 10 mL of HEMGENIX (see5). The total number of vials in each kit corresponds to the dosing requirement for the individual patient depending on the patient`s body weight [see Dosage and Administration (2.1)]. The customized kit is accompanied with patient`s specific identifier number (Lot) on the outer carton. Each HEMGENIX kit may contain different drug product lots.

Kit sizes and National Drug Codes (NDC) are provided in Table 5:

Table 5. HEMGENIX Multi-Vial Kits
Total Number of Vials per Kit | Patient Body Weight (kg) | Total Volume per Kit (mL) | NDC Number
10 | 46-50 | 100 | 0053-0100-10
11 | 51-55 | 110 | 0053-0110-11
12 | 56-60 | 120 | 0053-0120-12
13 | 61-65 | 130 | 0053-0130-13
14 | 66-70 | 140 | 0053-0140-14
15 | 71-75 | 150 | 0053-0150-15
16 | 76-80 | 160 | 0053-0160-16
17 | 81-85 | 170 | 0053-0170-17
18 | 86-90 | 180 | 0053-0180-18
19 | 91-95 | 190 | 0053-0190-19
20 | 96-100 | 200 | 0053-0200-20
21 | 101-105 | 210 | 0053-0210-21
22 | 106-110 | 220 | 0053-0220-22
23 | 111-115 | 230 | 0053-0230-23
24 | 116-120 | 240 | 0053-0240-24
25 | 121-125 | 250 | 0053-0250-25
26 | 126-130 | 260 | 0053-0260-26
27 | 131-135 | 270 | 0053-0270-27
28 | 136-140 | 280 | 0053-0280-28
29 | 141-145 | 290 | 0053-0290-29
30 | 146-150 | 300 | 0053-0300-30
31 | 151-155 | 310 | 0053-0310-31
32 | 156-160 | 320 | 0053-0320-32
33 | 161-165 | 330 | 0053-0330-33
34 | 166-170 | 340 | 0053-0340-34
35 | 171-175 | 350 | 0053-0350-35
36 | 176-180 | 360 | 0053-0360-36
37 | 181-185 | 370 | 0053-0370-37
38 | 186-190 | 380 | 0053-0380-38
39 | 191-195 | 390 | 0053-0390-39
40 | 196-200 | 400 | 0053-0400-40
41 | 201-205 | 410 | 0053-0410-41
42 | 206-210 | 420 | 0053-0420-42
43 | 211-215 | 430 | 0053-0430-43
44 | 216-220 | 440 | 0053-0440-44
45 | 221-225 | 450 | 0053-0450-45
46 | 226-230 | 460 | 0053-0460-46
47 | 231-235 | 470 | 0053-0470-47
48 | 236-240 | 480 | 0053-0480-48

16.2 Storage and Handling

- HEMGENIX is shipped at 2°C to 8°C (36°F to 46°F).
- Upon receipt, store HEMGENIX vials in a refrigerator at 2°C to 8°C (36°F to 46°F).
- Store HEMGENIX in the original carton until use.
- Protect HEMGENIX from light until time of dilution and administration.
- Do NOT FREEZE.

After dilution

- Once diluted, store HEMGENIX in the infusion bag protected from light.
- Store diluted HEMGENIX in the infusion bag at 15°C to 25°C (59°F to 77°F).
- Infuse the diluted product within 24 hours after the dose preparation [see Dosage and Administration (2.2)].

17 PATIENT COUNSELING INFORMATION

Inform patients that:

- Pre-infusion blood tests will be necessary to look for Factor IX inhibitors. If these exist, the patient may not be a good candidate for HEMGENIX [see Dosage and Administration (2)].
- Prior to HEMGENIX treatment, a liver ultrasound and elastography will be performed. Patients found to have pre-existing risk factors for hepatocellular carcinoma will be monitored annually in the 5 years following infusion [see Warnings and Precautions (5.4)].
- Infusion reactions can occur. Patients will be monitored during and for at least 3 hours following administration. If a reaction occurs, the infusion rate may be slowed or interrupted, then started at a slower rate [see Warnings and Precautions (5.1)].
- HEMGENIX can elevate certain liver enzymes. Weekly blood tests will be required to monitor for this for 3 months after treatment. Corticosteroid treatment may be necessary if this occurs [see Warnings and Precautions (5.2)].
- If post-infusion bleeding is not controlled or if bleeding returns, then blood tests will be performed for Factor IX activity and neutralizing Factor IX inhibitors [see Warnings and Precautions (5.5)].
- Vector distribution in blood (within the body), and vector shedding in semen and other excreta and secreta can occur post-infusion. It is not known how long this will continue. Patients should not donate blood, organs, tissues, or cells for transplantation [see Pharmacokinetics (12.3)].

Manufactured by:
Genezen MA, Inc.
113 Hartwell Avenue
Lexington, MA 02421 USA

Manufactured for:
CSL Behring LLC
King of Prussia, PA 19406 USA
US License No. 1767

Distributed by:
CSL Behring LLC
Kankakee, IL 60901 USA

For Patent information: www.cslbehring.com/products/patents (in-licensed from uniQure)

PRINCIPAL DISPLAY PANEL - 10 ml Vial Label

NDC 0053-0099-01
10 ml

etranacogene dezaparvovec-drlb
HEMGENIX®

1x10^13 genome copies/mL

Suspension for intravenous infusion
Single-dose vial
Do Not Shake
Dilute before use

Rx only

CSL Behring

PRINCIPAL DISPLAY PANEL - 10 ml Vial Carton

NDC 0053-0099-01

etranacogene dezaparvovec-drlb
HEMGENIX®

1 x 10^13 genome copies/mL
Suspension for intravenous infusion

Single-dose vial
1 x 10^13 genome copies/mL.
No US standard of potency.

Upon receipt store refrigerated at
2°C to 8°C (36°F to 46°F)

Do Not Freeze

Protect from Light

Do Not Shake

Dilute before use

See enclosed prescribing information
for dosage and directions for use

Rx only
CSL Behring

PRINCIPAL DISPLAY PANEL - Kit Carton

etranacogene dezaparvovec-drlb
HEMGENIX®

1 x 10^13 genome copies/mL
Suspension for intravenous infusion

Single-dose vial
Rx only

Upon receipt store refrigerated at 2°C to 8°C (36°F to 46°F)

Do Not Freeze

Protect from Light

Do Not Shake

Dilute before use

Manufactured by:
Genezen MA, Inc.
Lexington, MA 02421 USA

Manufactured for:
CSL Behring LLC
King of Prussia, PA 19406 USA
US License No. 1767

Distributed by:
CSL Behring LLC
Kankakee, IL 60901 USA

CSL Behring

PRINCIPAL DISPLAY PANEL - NDC: 0053-0100-10_ 46-50 KG KIT VARIABLE LABEL

etranacogene dezaparvovec-drlb
HEMGENIX®

Patient Weight: 46-50 kg

PRINCIPAL DISPLAY PANEL - NDC: 0053-0110-11_ 51-55 KG KIT VARIABLE LABEL

etranacogene dezaparvovec-drlb
HEMGENIX®

Patient Weight: 51-55 kg

PRINCIPAL DISPLAY PANEL - NDC: 0053-0120-12_ 56-60 KG KIT VARIABLE LABEL

etranacogene dezaparvovec-drlb
HEMGENIX®

Patient Weight: 56-60 kg

PRINCIPAL DISPLAY PANEL - NDC: 0053-0130-13_ 61-65 KG KIT VARIABLE LABEL

etranacogene dezaparvovec-drlb
HEMGENIX®

Patient Weight: 61-65 kg

PRINCIPAL DISPLAY PANEL - NDC: 0053-0140-14_ 66-70 KG KIT VARIABLE LABEL

etranacogene dezaparvovec-drlb
HEMGENIX®

Patient Weight: 66-70 kg

PRINCIPAL DISPLAY PANEL - NDC: 0053-0150-15_ 71-75 KG KIT VARIABLE LABEL

etranacogene dezaparvovec-drlb
HEMGENIX®

Patient Weight: 71-75 kg

PRINCIPAL DISPLAY PANEL - NDC: 0053-0160-16_ 76-80 KG KIT VARIABLE LABEL

etranacogene dezaparvovec-drlb
HEMGENIX®

Patient Weight: 76-80 kg

PRINCIPAL DISPLAY PANEL - NDC: 0053-0170-17_ 81-85 KG KIT VARIABLE LABEL

etranacogene dezaparvovec-drlb
HEMGENIX®

Patient Weight: 81-85 kg

PRINCIPAL DISPLAY PANEL - NDC: 0053-0180-18_ 86-90 KG KIT VARIABLE LABEL

etranacogene dezaparvovec-drlb
HEMGENIX®

Patient Weight: 86-90 kg

PRINCIPAL DISPLAY PANEL - NDC: 0053-0190-19_ 91-95 KG KIT VARIABLE LABEL

etranacogene dezaparvovec-drlb
HEMGENIX®

Patient Weight: 91-95 kg

PRINCIPAL DISPLAY PANEL - NDC: 0053-0200-20_ 96-100 KG KIT VARIABLE LABEL

etranacogene dezaparvovec-drlb
HEMGENIX®

Patient Weight: 96-100 kg

PRINCIPAL DISPLAY PANEL - NDC: 0053-0210-21_ 101-105 KG KIT VARIABLE LABEL

etranacogene dezaparvovec-drlb
HEMGENIX®

Patient Weight: 101-105 kg

PRINCIPAL DISPLAY PANEL - NDC: 0053-0220-22_ 106-110 KG KIT VARIABLE LABEL

etranacogene dezaparvovec-drlb
HEMGENIX®

Patient Weight: 106-110 kg

PRINCIPAL DISPLAY PANEL - NDC: 0053-0230-23_ 111-115 KG KIT VARIABLE LABEL

etranacogene dezaparvovec-drlb
HEMGENIX®

Patient Weight: 111-115 kg

PRINCIPAL DISPLAY PANEL - NDC: 0053-0240-24_ 116-120 KG KIT VARIABLE LABEL

etranacogene dezaparvovec-drlb
HEMGENIX®

Patient Weight: 116-120 kg

PRINCIPAL DISPLAY PANEL - NDC: 0053-0250-25_ 121-125 KG KIT VARIABLE LABEL

etranacogene dezaparvovec-drlb
HEMGENIX®

Patient Weight: 121-125 kg

PRINCIPAL DISPLAY PANEL - NDC: 0053-0260-26_ 126-130 KG KIT VARIABLE LABEL

etranacogene dezaparvovec-drlb
HEMGENIX®

Patient Weight: 126-130 kg

PRINCIPAL DISPLAY PANEL - NDC: 0053-0270-27_ 131-135 KG KIT VARIABLE LABEL

etranacogene dezaparvovec-drlb
HEMGENIX®

Patient Weight: 131-135 kg

PRINCIPAL DISPLAY PANEL - NDC: 0053-0280-28_ 136-140 KG KIT VARIABLE LABEL

etranacogene dezaparvovec-drlb
HEMGENIX®

Patient Weight: 136-140 kg

PRINCIPAL DISPLAY PANEL - NDC: 0053-0290-29_ 140-145 KG KIT VARIABLE LABEL

etranacogene dezaparvovec-drlb
HEMGENIX®

Patient Weight: 140-145 kg

PRINCIPAL DISPLAY PANEL - NDC: 0053-0300-30_ 146-150 KG KIT VARIABLE LABEL

etranacogene dezaparvovec-drlb
HEMGENIX®

Patient Weight: 146-150 kg

PRINCIPAL DISPLAY PANEL - NDC: 0053-0310-31_ 151-155 KG KIT VARIABLE LABEL

etranacogene dezaparvovec-drlb
HEMGENIX®

Patient Weight: 151-155 kg

PRINCIPAL DISPLAY PANEL - NDC: 0053-0320-32_ 156-160 KG KIT VARIABLE LABEL

etranacogene dezaparvovec-drlb
HEMGENIX®

Patient Weight: 156-160 kg

PRINCIPAL DISPLAY PANEL - NDC: 0053-0330-33_ 161-165 KG KIT VARIABLE LABEL

etranacogene dezaparvovec-drlb
HEMGENIX®

Patient Weight: 161-165 kg

PRINCIPAL DISPLAY PANEL - NDC: 0053-0340-34_ 166-170 KG KIT VARIABLE LABEL

etranacogene dezaparvovec-drlb
HEMGENIX®

Patient Weight: 166-170 kg

PRINCIPAL DISPLAY PANEL - NDC: 0053-0350-35_ 171-175 KG KIT VARIABLE LABEL

etranacogene dezaparvovec-drlb
HEMGENIX®

Patient Weight: 171-175 kg

PRINCIPAL DISPLAY PANEL - NDC: 0053-0360-36_ 176-180 KG KIT VARIABLE LABEL

etranacogene dezaparvovec-drlb
HEMGENIX®

Patient Weight: 176-180 kg

PRINCIPAL DISPLAY PANEL - NDC: 0053-0370-37_ 181-185 KG KIT VARIABLE LABEL

etranacogene dezaparvovec-drlb
HEMGENIX®

Patient Weight: 181-185 kg

PRINCIPAL DISPLAY PANEL - NDC: 0053-0380-38_ 186-190 KG KIT VARIABLE LABEL

etranacogene dezaparvovec-drlb
HEMGENIX®

Patient Weight: 186-190 kg

PRINCIPAL DISPLAY PANEL - NDC: 0053-0390-39_ 191-195 KG KIT VARIABLE LABEL

etranacogene dezaparvovec-drlb
HEMGENIX®

Patient Weight: 191-195 kg

PRINCIPAL DISPLAY PANEL - NDC: 0053-0400-40_ 196-200 KG KIT VARIABLE LABEL

etranacogene dezaparvovec-drlb
HEMGENIX®

Patient Weight: 196-200 kg

PRINCIPAL DISPLAY PANEL - NDC: 0053-0410-41_ 201-205 KG KIT VARIABLE LABEL

etranacogene dezaparvovec-drlb
HEMGENIX®

Patient Weight: 201-205 kg

PRINCIPAL DISPLAY PANEL - NDC: 0053-0420-42_ 206-210 KG KIT VARIABLE LABEL

etranacogene dezaparvovec-drlb
HEMGENIX®

Patient Weight: 206-210 kg

PRINCIPAL DISPLAY PANEL - NDC: 0053-0430-43_ 211-215 KG KIT VARIABLE LABEL

etranacogene dezaparvovec-drlb
HEMGENIX®

Patient Weight: 211-215 kg

PRINCIPAL DISPLAY PANEL - NDC: 0053-0440-44_ 216-220 KG KIT VARIABLE LABEL

etranacogene dezaparvovec-drlb
HEMGENIX®

Patient Weight: 216-220 kg

PRINCIPAL DISPLAY PANEL - NDC: 0053-0450-45_ 221-225 KG KIT VARIABLE LABEL

etranacogene dezaparvovec-drlb
HEMGENIX®

Patient Weight: 221-225 kg

PRINCIPAL DISPLAY PANEL - NDC: 0053-0460-46_ 226-230 KG KIT VARIABLE LABEL

etranacogene dezaparvovec-drlb
HEMGENIX®

Patient Weight: 226-230 kg

PRINCIPAL DISPLAY PANEL - NDC: 0053-0470-47_ 231-235 KG KIT VARIABLE LABEL

etranacogene dezaparvovec-drlb
HEMGENIX®

Patient Weight: 231-235 kg

PRINCIPAL DISPLAY PANEL - NDC: 0053-0480-48_ 236-240 KG KIT VARIABLE LABEL

etranacogene dezaparvovec-drlb
HEMGENIX®

Patient Weight: 236-240 kg